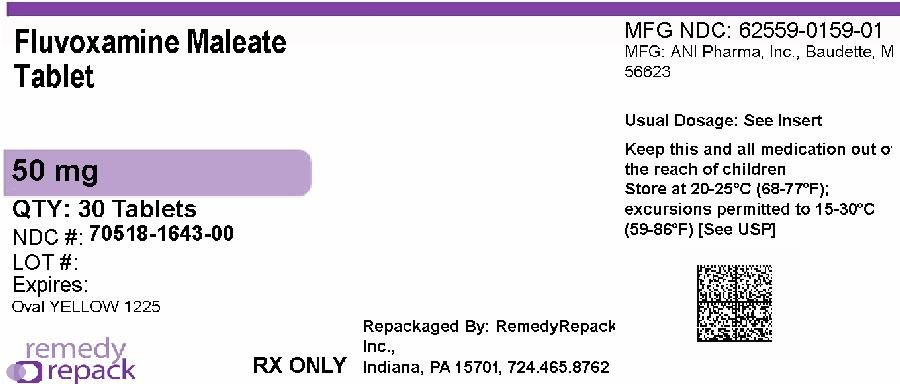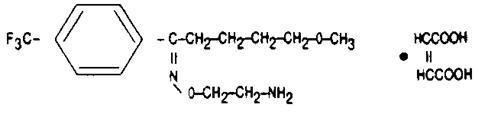 DRUG LABEL: fluvoxamine maleate
NDC: 70518-1643 | Form: TABLET, COATED
Manufacturer: REMEDYREPACK INC.
Category: prescription | Type: HUMAN PRESCRIPTION DRUG LABEL
Date: 20260126

ACTIVE INGREDIENTS: FLUVOXAMINE MALEATE 50 mg/1 1
INACTIVE INGREDIENTS: MANNITOL; POLYETHYLENE GLYCOL 3350; POLYVINYL ALCOHOL, UNSPECIFIED; SILICON DIOXIDE; SODIUM STEARYL FUMARATE; STARCH, CORN; STARCH, POTATO; TALC; TITANIUM DIOXIDE; FERRIC OXIDE YELLOW

HIGHLIGHTS OF PRESCRIBING INFORMATION

These highlights do not include all the information needed to use FLUVOXAMINE MALEATE TABLETS safely and effectively. See full prescribing information for FLUVOXAMINE MALEATE TABLETS.
FLUVOXAMINE MALEATE tablets, for oral use
Initial U.S. Approval: 1994

WARNING: SUICIDALITY AND ANTIDEPRESSANT DRUGS

WARNING: SUICIDALITY AND ANTIDEPRESSANTS

See full prescribing information for complete boxed warning.

Increased risk of suicidal thinking and behavior in children, adolescents, and young adults taking antidepressants for major depressive disorder and other psychiatric disorders. Fluvoxamine Maleate Tablets are not approved for use in pediatric patients except those with obsessive compulsive disorder (5.1).

1 INDICATIONS AND USAGE

Fluvoxamine Maleate Tablets are indicated for the treatment of obsessions and compulsions in patients with obsessive compulsive disorder (OCD) (1).

2 DOSAGE AND ADMINISTRATION

- Adults: Recommended starting dose is 50 mg at bedtime, with increases of 50 mg every 4 to 7 days as tolerated to maximum effect, not to exceed 300 mg/day. Daily doses over 100 mg should be divided. (2.1).
- Children and adolescents (8 -17 years): Recommended starting dose is 25 mg at bedtime, with increases of 25 mg every 4 to 7 days as tolerated to maximum effect, not to exceed 200 mg/day (8 -11 years) or 300 mg/day (12 -17 years). Daily doses over 50 mg should be divided (2.2).
- Hepatically impaired: Decreased clearance may require modified dose and titration (2.3).
- Extended treatment: Adjust dose to maintain lowest effective dose; reassess patients periodically (2.6).
- Discontinuation: Gradual dose reduction is recommended (2.7, 5.9).

3 DOSAGE FORMS AND STRENGTHS

- 50 mg Tablets (3)

4 CONTRAINDICATIONS

- Coadministration of tizanidine, thioridazine, alosteron, pimozide (4)
- Serotonin Syndrome and MAOIs:Do not use MAOIs intended to treat psychiatric disorders with Fluvoxamine Maleate Tablets or within 14 days of stopping treatment with Fluvoxamine Maleate Tablets. Do not use Fluvoxamine Maleate Tablets within 14 days of stopping an MAOI intended to treat psychiatric disorders. In addition, do not start Fluvoxamine Maleate Tablets in a patient who is being treated with linezolid or intravenous methylene blue (4)

5 WARNINGS AND PRECAUTIONS

- Suicidality:Monitor for clinical worsening and suicide risk (5.1).
- Bipolar disorder:Screen for bipolar disorder (5.1).
- Serotonin Syndrome:Serotonin syndrome has been reported with SSRIs and SNRIs, including Fluvoxamine Maleate Tablets, both when taken alone, but especially when co-administered with other serotonergic agents. If such symptoms occur, discontinue Fluvoxamine Maleate Tablets and serotonergic agents and initiate supportive treatment. If concomitant use of Fluvoxamine Maleate Tablets with other serotonergic drugs is clinically warranted, patients should be made aware of a potential increased risk for serotonin syndrome, particularly during treatment initiation and dose increases. (5.2).
- Angle Closure Glaucoma: Angle closure glaucoma has occurred in patients with untreated anatomically narrow angles treated with antidepressants (5.3).
- Other potentially important drug interactions. Benzodiazepines:Use with caution. Coadministration with diazepam is generally not advisable (5.8). Clozapine:Clozapine levels may be increased and produce orthostatic hypotension or seizures (5.8). Methadone:Coadministration may produce opioid intoxication. Discontinuation of fluvoxamine may produce opioid withdrawal (5.8). Mexiletine:Monitor serum mexiletine levels (5.8). Ramelteon:Should not be used in combination with fluvoxamine (5.8). Theophylline:Clearance decreased; reduce theophylline dose by one-third (5.8). Warfarin:Plasma concentrations increased and prothrombin times prolonged; monitor prothrombin time and adjust warfarin dose accordingly (5.8). Other Drugs Affecting Hemostasis:Increased risk of bleeding with concomitant use of NSAIDs, aspirin, or other drugs affecting coagulation (5.8, 5.10). See Contraindications(4).
- Discontinuation:Symptoms associated with discontinuation have been reported (5.9). Abrupt discontinuation not recommended. See Dosage And Administration(2.7).
- Activation of mania/hypomaniahas occurred (5.11).
- Seizures:Avoid administering fluvoxamine in patients with unstable epilepsy; monitor patients with controlled epilepsy; discontinue treatment if seizures occur or frequency increases (5.12).
- Hyponatremia:May occur with SSRIs and SNRIs, including Fluvoxamine Maleate Tablets. The elderly may be at increased risk. Consider discontinuing in patients with symptomatic hyponatremia (5.13).
- Concomitant Illness:Use caution in patients with diseases or conditions that affect hemodynamic response or metabolism (5.14). Patients with impaired liver function may require a lower starting dose and slower titration (2.3).
- Sexual Dysfunction:Fluvoxamine Maleate Tablets may cause symptoms of sexual dysfunction. (5.16)

6 ADVERSE REACTIONS

- Most common reactions in controlled trials with adult OCD and depression patients (incidence ≥ 5% and at least twice that for placebo) were nausea, somnolence, insomnia, asthenia, nervousness, dyspepsia, abnormal ejaculation, sweating, anorexia, tremor, and vomiting(6.2). Using the above rule, the following events were also identified: anorgasmia, decreased libido, dry mouth, rhinitis, taste perversion,and urinary frequencyin patients with OCD; and agitation, depression, dysmenorrhea, flatulence, hyperkinesia,and rashin pediatric patients with OCD.

To report SUSPECTED ADVERSE REACTIONS, contact ANI Pharmaceuticals, Inc. at 1-855-204-1431 or FDA at 1-800-FDA-1088 or www.fda.gov/medwatch.

7 DRUG INTERACTIONS

Drug Interactions (not described in Contraindicationsor Warnings And Precautions) include the following:

Drugs Inhibiting or Metabolized by Cytochrome P450: Fluvoxamine inhibits several cytochrome P450 isoenzymes (CYP1A2, CYP2C9, CYP3A4, and CYP2C19). Carbamazepine: Elevated carbamazepine levels and symptoms of toxicity with coadministration (7.2). Sumatriptan: Rare postmarketing reports of weakness, hyperreflexia, and incoordination following use of an SSRI and sumatriptan. Monitor appropriately if concomitant treatment is clinically warranted (7.2). Tacrine: Coadministration increased tacrine Cmaxand AUC five- and eight-fold and caused nausea, vomiting, sweating, and diarrhea (7.2). Tricyclic Antidepressants (TCAs): Coadministration significantly increased plasma TCA levels. Use caution; monitor plasma TCA levels; reduce TCA dose if indicated (7.2). Tryptophan: Severe vomiting with coadministration (7.2). Diltiazem: Bradycardia with coadministration (7.3). Propranolol or metoprolol: Reduce dose if coadministered and titrate more cautiously (7.3).

8 USE IN SPECIFIC POPULATIONS

Specific populations not discussed in Dosage and Administrationor Warnings and Precautionsinclude:

- Pregnancy: Third trimester use may increase risk for persistent pulmonary hypertension and symptoms of poor adaptation (respiratory distress, temperature instability, feeding difficulty, hypotonia, tremor, irritability) in the neonate (8.1).
- Pediatric: Monitor weight and growth; effects of long-term use on growth, cognitive behavioral development, and maturation have not been studied (8.4).
- Geriatric: Use of a lower starting dose may be warranted. Titrate slowly during initiation of therapy (2.3, 8.5).
- Smokers: Smokers had a 25% increase in fluvoxamine metabolism (7.4).

FULL PRESCRIBING INFORMATION

WARNING: SUICIDALITY AND ANTIDEPRESSANT DRUGS

Antidepressants increased the risk compared to placebo of suicidal thinking and behavior (suicidality) in children, adolescents, and young adults in short-term studies of major depressive disorder (MDD) and other psychiatric disorders. Anyone considering the use of Fluvoxamine Maleate Tablets or any other antidepressant in a child, adolescent, or young adult must balance this risk with the clinical need. Short-term studies did not show an increase in the risk of suicidality with antidepressants compared to placebo in adults beyond age 24; there was a reduction in risk with antidepressants compared to placebo in adults aged 65 and older. Depression and certain other psychiatric disorders are themselves associated with increases in the risk of suicide. Patients of all ages who are started on antidepressant therapy should be monitored appropriately and observed closely for clinical worsening, suicidality, or unusual changes in behavior. Families and caregivers should be advised of the need for close observation and communication with the prescriber. Fluvoxamine Maleate Tablets are not approved for use in pediatric patients except for patients with obsessive compulsive disorder (OCD) [see Warnings and Precautions (5.1)] .

1 INDICATIONS AND USAGE

1.1 Obsessive-Compulsive Disorder

Fluvoxamine Maleate Tablets are indicated for the treatment of obsessions and compulsions in patients with obsessive compulsive disorder (OCD), as defined in DSM-III-R or DSM-IV. The obsessions or compulsions cause marked distress, are time-consuming, or significantly interfere with social or occupational functioning.

Obsessive compulsive disorder is characterized by recurrent and persistent ideas, thoughts, impulses or images (obsessions) that are ego-dystonic and/or repetitive, purposeful, and intentional behaviors (compulsions) that are recognized by the person as excessive or unreasonable.

The efficacy of Fluvoxamine Maleate Tablets was established in four trials in outpatients with OCD: two 10-week trials in adults, one 10-week trial in pediatric patients (ages 8-17), and one maintenance trial in adults [see Clinical Studies (14)] .

2 DOSAGE AND ADMINISTRATION

2.1 Adults

The recommended starting dose for Fluvoxamine Maleate Tablets in adult patients is 50 mg, administered as a single daily dose at bedtime. In the controlled clinical trials establishing the effectiveness of Fluvoxamine Maleate Tablets in OCD, patients were titrated within a dose range of 100 to 300 mg/day. Consequently, the dose should be increased in 50 mg increments every 4 to 7 days, as tolerated, until maximum therapeutic benefit is achieved, not to exceed 300 mg per day. It is advisable that a total daily dose of more than 100 mg should be given in two divided doses. If the doses are not equal, the larger dose should be given at bedtime.

2.2 Pediatric Population (children and adolescents)

The recommended starting dose for Fluvoxamine Maleate Tablets in pediatric populations (ages 8-17 years) is 25 mg, administered as a single daily dose at bedtime. In a controlled clinical trial establishing the effectiveness of Fluvoxamine Maleate Tablets in OCD, pediatric patients (ages 8-17) were titrated within a dose range of 50 to 200 mg/day. Physicians should consider age and gender differences when dosing pediatric patients. The maximum dose in children up to age 11 should not exceed 200 mg/day. Therapeutic effect in female children may be achieved with lower doses. Dose adjustment in adolescents (up to the adult maximum dose of 300 mg) may be indicated to achieve therapeutic benefit. The dose should be increased in 25 mg increments every 4 to 7 days, as tolerated, until maximum therapeutic benefit is achieved. It is advisable that a total daily dose of more than 50 mg should be given in two divided doses. If the two divided doses are not equal, the larger dose should be given at bedtime.

2.3 Elderly or Hepatically Impaired Patients

Elderly patients and those with hepatic impairment have been observed to have a decreased clearance of fluvoxamine maleate. Consequently, it may be appropriate to modify the initial dose and the subsequent dose titration for these patient groups.

2.4 Switching a Patient To or From a Monoamine Oxidase Inhibitor (MAOI) Intended to Treat Psychiatric Disorders

At least 14 days should elapse between discontinuation of an MAOI intended to treat psychiatric disorders and initiation of therapy with Fluvoxamine Maleate Tablets. Conversely, at least 14 days should be allowed after stopping Fluvoxamine Maleate Tablets before starting an MAOI intended to treat psychiatric disorders [see Contraindications (4)] .

2.5 Use of Fluvoxamine Maleate Tablets with Other MAOIs such as Linezolid or Methylene Blue

Do not start Fluvoxamine Maleate Tablets in a patient who is being treated with linezolid or intravenous methylene blue because there is an increased risk of serotonin syndrome. In a patient who requires more urgent treatment of a psychiatric condition, other interventions, including hospitalization, should be considered [see Contraindications (4)] .

In some cases, a patient already receiving Fluvoxamine Maleate Tablets therapy may require urgent treatment with linezolid or intravenous methylene blue. If acceptable alternatives to linezolid or intravenous methylene blue treatment are not available and the potential benefits of linezolid or intravenous methylene blue treatment are judged to outweigh the risks of serotonin syndrome in a particular patient, Fluvoxamine Maleate Tablets should be stopped promptly, and linezolid or intravenous methylene blue can be administered. The patient should be monitored for symptoms of serotonin syndrome for two weeks or until 24 hours after the last dose of linezolid or intravenous methylene blue, whichever comes first. Therapy with Fluvoxamine Maleate Tablets may be resumed 24 hours after the last dose of linezolid or intravenous methylene blue [see Warnings and Precautions (5.2)] .

The risk of administering methylene blue by non-intravenous routes (such as oral tablets or by local injection) or in intravenous doses much lower than 1 mg/kg with Fluvoxamine Maleate Tablets is unclear. The clinician should, nevertheless, be aware of the possibility of emergent symptoms of serotonin syndrome with such use [see Warnings and Precautions (5.2)] .

2.6 Maintenance/Continuation Extended Treatment

It is generally agreed that obsessive compulsive disorder requires several months or longer of sustained pharmacologic therapy. The benefit of maintaining patients with OCD on Fluvoxamine Maleate Tablets after achieving a response for an average duration of about 4 weeks in a 10-week single-blind phase during which patients were titrated to effect was demonstrated in a controlled trial [see Clinical Trials (14.2)] . The physician who elects to use Fluvoxamine Maleate Tablets for extended periods should periodically re-evaluate the long-term usefulness of the drug for the individual patient.

2.7 Discontinuation of Treatment with Fluvoxamine Maleate Tablets

Symptoms associated with discontinuation of other SSRIs or SNRIs have been reported [see Warnings and Precautions (5.9)] . Patients should be monitored for these symptoms when discontinuing treatment. A gradual reduction in the dose rather than abrupt cessation is recommended whenever possible. If intolerable symptoms occur following a decrease in the dose or upon discontinuation of treatment, then resuming the previously prescribed dose may be considered. Subsequently, the physician may continue decreasing the dose but at a more gradual rate.

3 DOSAGE FORMS AND STRENGTHS

Fluvoxamine Maleate Tablets USP are available as:

Tablets 50 mg: scored, yellow, elliptical, film-coated (debossed “1225” on one side and scored on the other)

4 CONTRAINDICATIONS

Coadministration

Coadministration of tizanidine, thioridazine, alosetron, or pimozide with Fluvoxamine Maleate Tablets is contraindicated [see Warnings and Precautions (5.4, 5.5, 5.6, 5.7)] .

Serotonin Syndrome and Monoamine Oxidase Inhibitors (MAOIs)

The use of MAOIs intended to treat psychiatric disorders with Fluvoxamine Maleate Tablets or within 14 days of stopping treatment with Fluvoxamine Maleate Tablets is contraindicated because of an increased risk of serotonin syndrome. The use of Fluvoxamine Maleate Tablets within 14 days of stopping an MAOI intended to treat psychiatric disorders is also contraindicated [see Dosage and Administration (2.4), Warnings and Precautions (5.2)] .

Starting Fluvoxamine Maleate Tablets in a patient who is being treated with MAOIs such as linezolid or intravenous methylene blue is also contraindicated because of an increased risk of serotonin syndrome [see Dosage and Administration (2.5), Warnings and Precautions (5.2)] .

5 WARNINGS AND PRECAUTIONS

5.1 Clinical Worsening and Suicide Risk

Patients with major depressive disorder (MDD), both adult and pediatric, may experience worsening of their depression and/or the emergence of suicidal ideation and behavior (suicidality) or unusual changes in behavior, whether or not they are taking antidepressant medications, and this risk may persist until significant remission occurs. Suicide is a known risk of depression and certain other psychiatric disorders, and these disorders themselves are the strongest predictors of suicide. There has been a long-standing concern, however, that antidepressants may have a role in inducing worsening of depression and the emergence of suicidality in certain patients during the early phases of treatment. Pooled analyses of short-term placebo-controlled trials of antidepressant drugs (SSRIs and others) showed that these drugs increase the risk of suicidal thinking and behavior (suicidality) in children, adolescents, and young adults (ages 18-24) with major depressive disorder (MDD) and other psychiatric disorders. Short-term studies did not show an increase in the risk of suicidality with antidepressants compared to placebo in adults beyond age 24; there was a reduction with antidepressants compared to placebo in adults aged 65 and older.

The pooled analyses of placebo-controlled trials in children and adolescents with MDD, obsessive compulsive disorder (OCD), or other psychiatric disorders included a total of 24 short-term trials of 9 antidepressant drugs in over 4400 patients. The pooled analyses of placebo-controlled trials in adults with MDD or other psychiatric disorders included a total of 295 short-term trials (median duration of 2 months) of 11 antidepressant drugs in over 77,000 patients. There was considerable variation in risk of suicidality among drugs, but a tendency toward an increase in the younger patients for almost all drugs studied. There were differences in absolute risk of suicidality across the different indications, with the highest incidence in MDD. The risk differences (drug vs placebo), however, were relatively stable within age strata and across indications. These risk differences (drug-placebo difference in the number of cases of suicidality per 1000 patients treated) are provided in Table 1.

TABLE 1 DRUG-PLACEBO DIFFERENCES IN NUMBER OF CASES OF SUICIDALITY PER 1000 PATIENTS TREATED
Age Range | Increases Compared to Placebo
<18 | 14 Additional Cases
18-24 | 5 Additional Cases
Age Range | Decreases Compared to Placebo
25-64 | 1 Fewer Case
≥65 | 6 Fewer Cases

No suicides occurred in any of the pediatric trials. There were suicides in the adult trials, but the number was not sufficient to reach any conclusion about the drug effect on suicide.

It is unknown whether the suicidality risk extends to longer-term use, i.e., beyond several months. However, there is substantial evidence from placebo-controlled maintenance trials in adults with depression that the use of antidepressants can delay the recurrence of depression.

All patients being treated with antidepressants for any indication should be monitored appropriately and observed closely for clinical worsening, suicidality, and unusual changes in behavior, especially during the initial few months of a course of drug therapy, or at times of dose changes, either increases or decreases.

The following symptoms, anxiety, agitation, panic attacks, insomnia, irritability, hostility, aggressiveness, impulsivity, akathisia (psychomotor restlessness), hypomania, and mania, have been reported in adult and pediatric patients being treated with antidepressants for major depressive disorder as well as for other indications, both psychiatric and nonpsychiatric. Although a causal link between the emergence of such symptoms and either the worsening of depression and/or the emergence of suicidal impulses has not been established, there is concern that such symptoms may represent precursors to emerging suicidality.

Consideration should be given to changing the therapeutic regimen, including possibly discontinuing the medication, in patients whose depression is persistently worse, or who are experiencing emergent suicidality or symptoms that might be precursors to worsening depression or suicidality, especially if these symptoms are severe, abrupt in onset, or were not part of the patient’s presenting symptoms.

If the decision has been made to discontinue treatment, medication should be tapered, as rapidly as is feasible, but with recognition that abrupt discontinuation can be associated with certain symptoms and risks [see Dosage and Administration (2.7)].

Families and caregivers of patients being treated with antidepressants for major depressive disorder or other indications, both psychiatric and nonpsychiatric, should be alerted about the need to monitor patients for the emergence of agitation, irritability, unusual changes in behavior, and the other symptoms described above, as well as the emergence of suicidality, and to report such symptoms immediately to healthcare providers. Such monitoring should include daily observation by families and caregivers.Prescriptions for Fluvoxamine Maleate Tablets should be written for the smallest quantity of tablets consistent with good patient management, in order to reduce the risk of overdose.

Screening Patients for Bipolar Disorder:A major depressive episode may be the initial presentation of bipolar disorder. It is generally believed (though not established in controlled trials) that treating such an episode with an antidepressant alone may increase the likelihood of precipitation of a mixed/manic episode in patients at risk for bipolar disorder. Whether any of the symptoms described above represent such a conversion is unknown. However, prior to initiating treatment with an antidepressant, patients with depressive symptoms should be adequately screened to determine if they are at risk for bipolar disorder; such screening should include a detailed psychiatric history, including a family history of suicide, bipolar disorder, and depression. It should be noted that Fluvoxamine Maleate Tablets are not approved for use in treating bipolar depression.

5.2 Serotonin Syndrome

Selective serotonin reuptake inhibitors (SSRIs), including Fluvoxamine Maleate Tablets, can precipitate serotonin syndrome, a potentially life-threatening condition. The risk is increased with concomitant use of other serotonergic drugs (including triptans, tricyclic antidepressants, fentanyl, meperidine, methadone, lithium, tramadol, tryptophan, buspirone, amphetamines, and St. John's Wort) and with drugs that impair metabolism of serotonin, i.e., MAOIs [see Contraindications (4), Drug Interactions (7.1)] . Serotonin syndrome can also occur when these drugs are used alone.

Serotonin syndrome signs and symptoms may include mental status changes (e.g., agitation, hallucinations, delirium, and coma), autonomic instability (e.g., tachycardia, labile blood pressure, dizziness, diaphoresis, flushing, hyperthermia), neuromuscular symptoms (e.g., tremor, rigidity, myoclonus, hyperreflexia, incoordination), seizures, and gastrointestinal symptoms (e.g., nausea, vomiting, diarrhea). Patients should be monitored for the emergence of serotonin syndrome.

The concomitant use of Fluvoxamine Maleate Tablets with MAOIs is contraindicated. In addition, do not initiate Fluvoxamine Maleate Tablets in a patient being treated with MAOIs such as linezolid or intravenous methylene blue. No reports involved the administration of methylene blue by other routes (such as oral tablets or local tissue injection). If it is necessary to initiate treatment with an MAOI such as linezolid or intravenous methylene blue in a patient taking Fluvoxamine Maleate Tablets, discontinue Fluvoxamine Maleate Tablets before initiating treatment with the MAOI [see Contraindications (4), Drug Interactions (7.2)] .

Monitor all patients taking Fluvoxamine Maleate Tablets for the emergence of serotonin syndrome. Discontinue treatment with Fluvoxamine Maleate Tablets and any concomitant serotonergic agents immediately if the above symptoms occur, and initiate supportive symptomatic treatment. If concomitant use of Fluvoxamine Maleate Tablets with other serotonergic drugs is clinically warranted, inform patients of the increased risk for serotonin syndrome and monitor for symptoms.

5.3 Angle Closure Glaucoma

The pupillary dilation that occurs following use of many antidepressant drugs including Fluvoxamine Maleate Tablets may trigger an angle closure attack in a patient with anatomically narrow angles who do not have a patent iridectomy.

5.4 Potential Thioridazine Interaction

The effect of fluvoxamine (25 mg b.i.d. for one week) on thioridazine steady-state concentrations was evaluated in 10 male inpatients with schizophrenia. Concentrations of thioridazine and its two active metabolites, mesoridazine and sulforidazine, increased threefold following coadministration of fluvoxamine.

Thioridazine administration produces a dose-related prolongation of the QTc interval, which is associated with serious ventricular arrhythmias, such as torsades de pointes-type arrhythmias, and sudden death. It is likely that this experience underestimates the degree of risk that might occur with higher doses of thioridazine. Moreover, the effect of fluvoxamine may be even more pronounced when it is administered at higher doses.

Therefore, fluvoxamine and thioridazine should not be coadministered [see Contraindications (4)] .

5.5 Potential Tizanidine Interaction

Fluvoxamine is a potent inhibitor of CYP1A2 and tizanidine is a CYP1A2 substrate. The effect of fluvoxamine (100 mg daily for 4 days) on the pharmacokinetics and pharmacodynamics of a single 4 mg dose of tizanidine has been studied in 10 healthy male subjects. Tizanidine Cmaxwas increased approximately 12-fold (range 5-fold to 32-fold), elimination half-life was increased by almost 3-fold, and AUC increased 33-fold (range 14-fold to 103-fold). The mean maximal effect on blood pressure was a 35 mm Hg decrease in systolic blood pressure, a 20 mm Hg decrease in diastolic blood pressure, and a 4 beat/min decrease in heart rate. Drowsiness was significantly increased and performance on the psychomotor task was significantly impaired. Fluvoxamine and tizanidine should not be used together [see Contraindications (4)] .

5.6 Potential Pimozide Interaction

Pimozide is metabolized by the cytochrome P4503A4 isoenzyme, and it has been demonstrated that ketoconazole, a potent inhibitor of CYP3A4, blocks the metabolism of this drug, resulting in increased plasma concentrations of parent drug. An increased plasma concentration of pimozide causes QT prolongation and has been associated with torsades de pointes-type ventricular tachycardia, sometimes fatal. As noted below, a substantial pharmacokinetic interaction has been observed for fluvoxamine in combination with alprazolam, a drug that is known to be metabolized by CYP3A4. Although it has not been definitively demonstrated that fluvoxamine is a potent CYP3A4 inhibitor, it is likely to be, given the substantial interaction of fluvoxamine with alprazolam. Consequently, it is recommended that fluvoxamine not be used in combination with pimozide [see Contraindications (4)] .

5.7 Potential Alosetron Interaction

Because alosetron is metabolized by a variety of hepatic CYP drug metabolizing enzymes, inducers or inhibitors of these enzymes may change the clearance of alosetron. Fluvoxamine is a known potent inhibitor of CYP1A2 and also inhibits CYP3A4, CYP2C9, and CYP2C19. In a pharmacokinetic study, 40 healthy female subjects received fluvoxamine in escalating doses from 50 mg to 200 mg a day for 16 days, with coadministration of alosetron 1 mg on the last day. Fluvoxamine increased mean alosetron plasma concentration (AUC) approximately 6-fold and prolonged the half-life by approximately 3-fold. [See Contraindications (4) and LotronexTM(alosetron) package insert] .

5.8 Other Potentially Important Drug Interactions

Benzodiazepines:Benzodiazepines metabolized by hepatic oxidation (e.g., alprazolam, midazolam, triazolam, etc.) should be used with caution because the clearance of these drugs is likely to be reduced by fluvoxamine. The clearance of benzodiazepines metabolized by glucuronidation (e.g., lorazepam, oxazepam, temazepam) is unlikely to be affected by fluvoxamine.

Alprazolam- When fluvoxamine maleate (100 mg q.d.) and alprazolam (1 mg q.i.d.) were coadministered to steady state, plasma concentrations and other pharmacokinetic parameters (AUC, Cmax, T½) of alprazolam were approximately twice those observed when alprazolam was administered alone; oral clearance was reduced by about 50%. The elevated plasma alprazolam concentrations resulted in decreased psychomotor performance and memory. This interaction, which has not been investigated using higher doses of fluvoxamine, may be more pronounced if a 300 mg daily dose is coadministered, particularly since fluvoxamine exhibits non-linear pharmacokinetics over the dosage range 100-300 mg. If alprazolam is coadministered with Fluvoxamine Maleate Tablets, the initial alprazolam dosage should be at least halved and titration to the lowest effective dose is recommended. No dosage adjustment is required for Fluvoxamine Maleate Tablets.

Diazepam- The coadministration of Fluvoxamine Maleate Tablets and diazepam is generally not advisable. Because fluvoxamine reduces the clearance of both diazepam and its active metabolite, N-desmethyldiazepam, there is a strong likelihood of substantial accumulation of both species during chronic coadministration.

Evidence supporting the conclusion that it is inadvisable to coadminister fluvoxamine and diazepam is derived from a study in which healthy volunteers taking 150 mg/day of fluvoxamine were administered a single oral dose of 10 mg of diazepam. In these subjects (N=8), the clearance of diazepam was reduced by 65% and that of N-desmethyldiazepam to a level that was too low to measure over the course of the 2 week long study.

It is likely that this experience significantly underestimates the degree of accumulation that might occur with repeated diazepam administration. Moreover, as noted with alprazolam, the effect of fluvoxamine may even be more pronounced when it is administered at higher doses.

Accordingly, diazepam and fluvoxamine should not ordinarily be coadministered.

Clozapine- Elevated serum levels of clozapine have been reported in patients taking fluvoxamine maleate and clozapine. Since clozapine-related seizures and orthostatic hypotension appear to be dose related, the risk of these adverse events may be higher when fluvoxamine and clozapine are coadministered. Patients should be closely monitored when fluvoxamine maleate and clozapine are used concurrently.

Methadone:Significantly increased methadone (plasma level:dose) ratios have been reported when fluvoxamine maleate was administered to patients receiving maintenance methadone treatment, with symptoms of opioid intoxication in one patient. Opioid withdrawal symptoms were reported following fluvoxamine maleate discontinuation in another patient.

Mexiletine:The effect of steady-state fluvoxamine (50 mg b.i.d. for 7 days) on the single dose pharmacokinetics of mexiletine (200 mg) was evaluated in 6 healthy Japanese males. The clearance of mexiletine was reduced by 38% following coadministration with fluvoxamine compared to mexiletine alone. If fluvoxamine and mexiletine are coadministered, serum mexiletine levels should be monitored.

Ramelteon:When fluvoxamine 100 mg twice daily was administered for 3 days prior to single-dose coadministration of ramelteon 16 mg and fluvoxamine, the AUC for ramelteon increased approximately 190-fold and the Cmaxincreased approximately 70-fold compared to ramelteon administered alone. Ramelteon should not be used in combination with fluvoxamine.

Theophylline:The effect of steady-state fluvoxamine (50 mg bid) on the pharmacokinetics of a single dose of theophylline (375 mg as 442 mg aminophylline) was evaluated in 12 healthy non-smoking, male volunteers. The clearance of theophylline was decreased approximately 3-fold. Therefore, if theophylline is coadministered with fluvoxamine maleate, its dose should be reduced to one-third of the usual daily maintenance dose and plasma concentrations of theophylline should be monitored. No dosage adjustment is required for Fluvoxamine Maleate Tablets.

Warfarin and Other Drugs That Interfere With Hemostasis (NSAIDs, Aspirin, etc.):Serotonin release by platelets plays an important role in hemostasis. Epidemiological studies of the case-control and cohort design have demonstrated an association between use of psychotropic drugs that interfere with serotonin reuptake and the occurrence of upper gastrointestinal bleeding. These studies have also shown that concurrent use of an NSAID or aspirin may potentiate this risk of bleeding. Thus, patients should be cautioned about the use of such drugs concurrently with fluvoxamine [see Warnings and Precautions (5.10)] .

Warfarin- When fluvoxamine maleate (50 mg t.i.d.) was administered concomitantly with warfarin for two weeks, warfarin plasma concentrations increased by 98% and prothrombin times were prolonged. Thus patients receiving oral anticoagulants and Fluvoxamine Maleate Tablets should have their prothrombin time monitored and their anticoagulant dose adjusted accordingly. No dosage adjustment is required for Fluvoxamine Maleate Tablets.

5.9 Discontinuation of Treatment with Fluvoxamine Maleate Tablets

During marketing of Fluvoxamine Maleate Tablets and other SSRIs and SNRIs (serotonin and norepinephrine reuptake inhibitors), there have been spontaneous reports of adverse events occurring upon discontinuation of these drugs, particularly when abrupt, including the following: dysphoric mood, irritability, agitation, dizziness, sensory disturbances (e.g., paresthesias, such as electric shock sensations), anxiety, confusion, headache, lethargy, emotional lability, insomnia and hypomania. While these events are generally self-limiting, there have been reports of serious discontinuation symptoms.

Patients should be monitored for these symptoms when discontinuing treatment with Fluvoxamine Maleate Tablets. A gradual reduction in the dose rather than abrupt cessation is recommended whenever possible. If intolerable symptoms occur following a decrease in the dose or upon discontinuation of treatment, then resuming the previously prescribed dose may be considered. Subsequently, the physician may continue decreasing the dose but at a more gradual rate [see Dosage and Administration (2.7)].

5.10 Increased Risk of Bleeding

SSRIs and SNRIs, including Fluvoxamine Maleate Tablets, may increase the risk of bleeding events. Concomitant use of aspirin, nonsteroidal anti-inflammatory drugs, warfarin, and other anticoagulants may add to this risk. Case reports and epidemiological studies (case-control and cohort design) have demonstrated an association between use of drugs that interfere with serotonin reuptake and the occurrence of gastrointestinal bleeding. Based on data from the published observational studies, exposure to SSRIs, particularly in the month before delivery, has been associated with a less than 2-fold increase in the risk of postpartum hemorrhage [see Use in Specific Populations (8.1)] . Bleeding events related to SSRIs and SNRIs have ranged from ecchymoses, hematomas, epistaxis, and petechiae to life-threatening hemorrhages.

Patients should be cautioned about the increased risk of bleeding associated with the concomitant use of Fluvoxamine Maleate Tablets and NSAIDs, aspirin, or other drugs that affect coagulation [see Warnings and Precautions (5.8)] .

5.11 Activation of Mania/Hypomania

During premarketing studies involving primarily depressed patients, hypomania or mania occurred in approximately 1% of patients treated with fluvoxamine. In a ten week pediatric OCD study, 2 out of 57 patients (4%) treated with fluvoxamine experienced manic reactions, compared to none of 63 placebo patients. Activation of mania/hypomania has also been reported in a small proportion of patients with major affective disorder who were treated with other marketed antidepressants. As with all antidepressants, Fluvoxamine Maleate Tablets should be used cautiously in patients with a history of mania.

5.12 Seizures

During premarketing studies, seizures were reported in 0.2% of fluvoxamine-treated patients. Caution is recommended when the drug is administered to patients with a history of convulsive disorders. Fluvoxamine should be avoided in patients with unstable epilepsy and patients with controlled epilepsy should be carefully monitored. Treatment with fluvoxamine should be discontinued if seizures occur or if seizure frequency increases.

5.13 Hyponatremia

Hyponatremia may occur as a result of treatment with SSRIs and SNRIs, including Fluvoxamine Maleate Tablets. In many cases, this hyponatremia appears to be the result of the syndrome of inappropriate antidiuretic hormone (SIADH). Cases with serum sodium lower than 110 mmol/L have been reported. Elderly patients may be at greater risk of developing hyponatremia with SSRIs and SNRIs [see Use in Specific Populations (8.5)] . Also, patients taking diuretics or who are otherwise volume depleted may be at greater risk. Discontinuation of Fluvoxamine Maleate Tablets should be considered in patients with symptomatic hyponatremia and appropriate medical intervention should be instituted.

Signs and symptoms of hyponatremia include headache, difficulty concentrating, memory impairment, confusion, weakness, and unsteadiness, which may lead to falls. Signs and symptoms associated with more severe and/or acute cases have included hallucination, syncope, seizure, coma, respiratory arrest, and death.

5.14 Use in Patients with Concomitant Illness

Closely monitored clinical experience with Fluvoxamine Maleate Tablets in patients with concomitant systemic illness is limited. Caution is advised in administering Fluvoxamine Maleate Tablets to patients with diseases or conditions that could affect hemodynamic responses or metabolism.

Fluvoxamine Maleate Tablets have not been evaluated or used to any appreciable extent in patients with a recent history of myocardial infarction or unstable heart disease. Patients with these diagnoses were systematically excluded from many clinical studies during the product's premarketing testing. Evaluation of the electrocardiograms for patients with depression or OCD who participated in premarketing studies revealed no differences between fluvoxamine and placebo in the emergence of clinically important ECG changes.

Patients with Hepatic Impairment -In patients with liver dysfunction, fluvoxamine clearance was decreased by approximately 30%. Patients with liver dysfunction should begin with a low dose of Fluvoxamine Maleate Tablets and increase it slowly with careful monitoring.

5.15 Laboratory Tests

There are no specific laboratory tests recommended.

5.16 Sexual Dysfunction

Use of SSRIs, including Fluvoxamine Maleate Tablets, may cause symptoms of sexual dysfunction [see Adverse Reactions (6.4)] . In male patients, SSRI use may result in ejaculatory delay or failure, decreased libido, and erectile dysfunction. In female patients, SSRI use may result in decreased libido and delayed or absent orgasm.

It is important for prescribers to inquire about sexual function prior to initiation of Fluvoxamine Maleate Tablets and to inquire specifically about changes in sexual function during treatment, because sexual function may not be spontaneously reported. When evaluating changes in sexual function, obtaining a detailed history (including timing of symptom onset) is important because sexual symptoms may have other causes, including the underlying psychiatric disorder. Discuss potential management strategies to support patients in making informed decisions about treatment.

6 ADVERSE REACTIONS

Because clinical trials are conducted under widely varying conditions, adverse reaction rates observed in the clinical trials of a drug cannot be directly compared to rates in the clinical trials of another drug and may not reflect the rates observed in practice.

6.1 Adverse Reactions Leading to Treatment Discontinuation

Of the 1087 OCD and depressed patients treated with fluvoxamine maleate in controlled clinical trials in North America, 22% discontinued due to an adverse reaction. Adverse reactions that led to discontinuation in at least 2% of fluvoxamine maleate-treated patients in these trials were: nausea (9%), insomnia (4%), somnolence (4%), headache (3%), and asthenia, vomiting, nervousness, agitation, and dizziness (2% each).

6.2 Incidence in Controlled Trials

Commonly Observed Adverse Reactions in Controlled Clinical Trials:Fluvoxamine Maleate Tablets have been studied in 10-week short-term controlled trials of OCD (N=320) and depression (N=1350). In general, adverse reaction rates were similar in the two data sets as well as in the pediatric OCD study. The most commonly observed adverse reactions associated with the use of Fluvoxamine Maleate Tablets and likely to be drug-related (incidence of 5% or greater and at least twice that for placebo) derived from Table 2were: nausea, somnolence, insomnia, asthenia, nervousness, dyspepsia, abnormal ejaculation, sweating, anorexia, tremor,and vomiting.In a pool of two studies involving only patients with OCD, the following additional reactions were identified using the above rule: anorgasmia, decreased libido, dry mouth, rhinitis, taste perversion,and urinary frequency.In a study of pediatric patients with OCD, the following additional reactions were identified using the above rule: agitation, depression, dysmenorrhea, flatulence, hyperkinesia,and rash.

Adverse Reactions Occurring at an Incidence of 1%:Table 2enumerates adverse reactions that occurred in adults at a frequency of 1% or more, and were more frequent than in the placebo group, among patients treated with Fluvoxamine Maleate Tablets in two short-term placebo controlled OCD trials (10 week) and depression trials (6 week) in which patients were dosed in a range of generally 100 to 300 mg/day. This table shows the percentage of patients in each group who had at least one occurrence of a reaction at some time during their treatment. Reported adverse reactions were classified using a standard COSTART-based Dictionary terminology.

The prescriber should be aware that these figures cannot be used to predict the incidence of side effects in the course of usual medical practice where patient characteristics and other factors may differ from those that prevailed in the clinical trials. Similarly, the cited frequencies cannot be compared with figures obtained from other clinical investigations involving different treatments, uses, and investigators. The cited figures, however, do provide the prescribing physician with some basis for estimating the relative contribution of drug and non-drug factors to the side-effect incidence rate in the population studied.

TABLE 2 TREATMENT-EMERGENT ADVERSE REACTION INCIDENCE RATES BY BODY SYSTEM IN ADULT OCD AND DEPRESSION POPULATIONS COMBINED^1
BODY SYSTEM/ADVERSE REACTION | Percentage of Patients Reporting Reaction
BODY SYSTEM/ADVERSE REACTION | FLUVOXAMINE N=892 | PLACEBO N=778
BODY AS WHOLE
Headache | 22 | 20
Asthenia | 14 | 6
Flu Syndrome | 3 | 2
Chills | 2 | 1
CARDIOVASCULAR
Palpitations | 3 | 2
DIGESTIVE SYSTEM
Nausea | 40 | 14
Diarrhea | 11 | 7
Constipation | 10 | 8
Dyspepsia | 10 | 5
Anorexia | 6 | 2
Vomiting | 5 | 2
Flatulence | 4 | 3
Tooth Disorder^2 | 3 | 1
Dysphagia | 2 | 1
NERVOUS SYSTEM
Somnolence | 22 | 8
Insomnia | 21 | 10
Dry Mouth | 14 | 10
Nervousness | 12 | 5
Dizziness | 11 | 6
Tremor | 5 | 1
Anxiety | 5 | 3
Vasodilatation^3 | 3 | 1
Hypertonia | 2 | 1
Agitation | 2 | 1
Decreased Libido | 2 | 1
Depression | 2 | 1
CNS Stimulation | 2 | 1
RESPIRATORY SYSTEM
Upper Respiratory Infection | 9 | 5
Dyspnea | 2 | 1
Yawn | 2 | 0
SKIN
Sweating | 7 | 3
SPECIAL SENSES
Taste Perversion | 3 | 1
Amblyopia^4 | 3 | 2
UROGENITAL
Abnormal Ejaculation^5,6 | 8 | 1
Urinary Frequency | 3 | 2
Impotence^6 | 2 | 1
Anorgasmia | 2 | 0
Urinary Retention | 1 | 0
^1Reactions for which fluvoxamine maleate incidence was equal to or less than placebo are not listed in the table above.
^2Includes “toothache,” “tooth extraction and abscess,” and “caries.”
^3Mostly feeling warm, hot, or flushed.
^4Mostly “blurred vision.”
^5Mostly “delayed ejaculation.”
^6Incidence based on number of male patients.

Adverse Reactions in OCD Placebo Controlled Studies Which are Markedly Different (defined as at least a two-fold difference) in Rate from the Pooled Reaction Rates in OCD and Depression Placebo Controlled Studies:The reactions in OCD studies with a two-fold decrease in rate compared to reaction rates in OCD and depression studies were dysphagia and amblyopia (mostly blurred vision). Additionally, there was an approximate 25% decrease in nausea.

The reactions in OCD studies with a two-fold increase in rate compared to reaction rates in OCD and depression studies were: asthenia, abnormal ejaculation (mostly delayed ejaculation), anxiety, rhinitis, anorgasmia (in males), depression, libido decreased, pharyngitis, agitation, impotence, myoclonus/twitch, thirst, weight loss, leg cramps, myalgia,and urinary retention.These reactions are listed in order of decreasing rates in the OCD trials.

6.3 Other Adverse Reactions in OCD Pediatric Population

In pediatric patients (N=57) treated with Fluvoxamine Maleate Tablets, the overall profile of adverse reactions was generally similar to that seen in adult studies, as shown in Table 2. However, the following adverse reactions, not appearing in Table 2, were reported in two or more of the pediatric patients and were more frequent with Fluvoxamine Maleate Tablets than with placebo: cough increase, dysmenorrhea, ecchymosis, emotional lability, epistaxis, hyperkinesia, manic reaction, rash, sinusitis, and weight decrease.

6.4 Male and Female Sexual Dysfunction with SSRIs

Although changes in sexual desire, sexual performance and sexual satisfaction often occur as manifestations of a psychiatric disorder and with aging, they may also be a consequence of pharmacologic treatment. In particular, some evidence suggests that selective serotonin reuptake inhibitors (SSRIs), can cause such untoward sexual experiences.

Reliable estimates of the incidence and severity of untoward experiences involving sexual desire, performance and satisfaction are difficult to obtain, however, in part because patients and physicians may be reluctant to discuss them. Accordingly, estimates of the incidence of untoward sexual experience and performance cited in product labeling are likely to underestimate their actual incidence.

Table 3displays the incidence of sexual side effects reported by at least 2% of patients taking Fluvoxamine Maleate Tablets in placebo-controlled trials in depression and OCD.

TABLE 3 PERCENTAGE OF PATIENTS REPORTING SEXUAL ADVERSE REACTIONS IN ADULT PLACEBO-CONTROLLED TRIALS IN OCD AND DEPRESSION
 | Fluvoxamine Maleate Tablets; N=892 | Placebo; N=778
Abnormal Ejaculation* | 8% | 1%
Impotence* | 2% | 1%
Decreased Libido | 2% | 1%
Anorgasmia | 2% | 0%
*Based on the number of male patients.

There are no adequate and well-controlled studies examining sexual dysfunction with fluvoxamine treatment.

Fluvoxamine treatment has been associated with several cases of priapism. In those cases with a known outcome, patients recovered without sequelae and upon discontinuation of fluvoxamine.

While it is difficult to know the precise risk of sexual dysfunction associated with the use of SSRIs, physicians should routinely inquire about such possible side effects.

6.5 Vital Sign Changes

Comparisons of fluvoxamine maleate and placebo groups in separate pools of short-term OCD and depression trials on (1) median change from baseline on various vital signs variables and on (2) incidence of patients meeting criteria for potentially important changes from baseline on various vital signs variables revealed no important differences between fluvoxamine maleate and placebo.

6.6 Laboratory Changes

Comparisons of fluvoxamine maleate and placebo groups in separate pools of short-term OCD and depression trials on (1) median change from baseline on various serum chemistry, hematology, and urinalysis variables and on (2) incidence of patients meeting criteria for potentially important changes from baseline on various serum chemistry, hematology, and urinalysis variables revealed no important differences between fluvoxamine maleate and placebo.

6.7 ECG Changes

Comparisons of fluvoxamine maleate and placebo groups in separate pools of short-term OCD and depression trials on (1) mean change from baseline on various ECG variables and on (2) incidence of patients meeting criteria for potentially important changes from baseline on various ECG variables revealed no important differences between fluvoxamine maleate and placebo.

6.8 Other Reactions Observed During the Premarketing Evaluation of Fluvoxamine Maleate Tablets

During premarketing clinical trials conducted in North America and Europe, multiple doses of fluvoxamine maleate were administered for a combined total of 2737 patient exposures in patients suffering OCD or Major Depressive Disorder. Untoward reactions associated with this exposure were recorded by clinical investigators using descriptive terminology of their own choosing. Consequently, it is not possible to provide a meaningful estimate of the proportion of individuals experiencing adverse reactions without first grouping similar types of untoward reactions into a limited (i.e., reduced) number of standard reaction categories.

In the tabulations which follow, a standard COSTART-based Dictionary terminology has been used to classify reported adverse reactions. If the COSTART term for a reaction was so general as to be uninformative, it was replaced with a more informative term. The frequencies presented, therefore, represent the proportion of the 2737 patient exposures to multiple doses of fluvoxamine maleate who experienced a reaction of the type cited on at least one occasion while receiving fluvoxamine maleate. All reported reactions are included in the list below, with the following exceptions: 1) those reactions already listed in Table 2, which tabulates incidence rates of common adverse experiences in placebo-controlled OCD and depression clinical trials, are excluded; 2) those reactions for which a drug cause was not considered likely are omitted; 3) reactions for which the COSTART term was too vague to be clinically meaningful and could not be replaced with a more informative term; and 4) reactions which were reported in only one patient and judged to not be potentially serious are not included. It is important to emphasize that, although the reactions reported did occur during treatment with fluvoxamine maleate, a causal relationship to fluvoxamine maleate has not been established.

Reactions are further classified within body system categories and enumerated in order of decreasing frequency using the following definitions: frequent adverse reactions are defined as those occurring on one or more occasions in at least 1/100 patients; infrequent adverse reactions are those occurring between 1/100 and 1/1000 patients; and rare adverse reactions are those occurring in less than 1/1000 patients.

Body as a Whole– Frequent:malaise; Infrequent:photosensitivity reaction and suicide attempt.

Cardiovascular System– Frequent:syncope.

Digestive System– Infrequent:gastrointestinal hemorrhage and melena; Rare:hematemesis.

Hemic and Lymphatic Systems– Infrequent:anemia and ecchymosis; Rare:purpura.

Metabolic and Nutritional Systems– Frequent:weight gain and weight loss.

Nervous System– Frequent:hyperkinesia, manic reaction, and myoclonus; Infrequent:abnormal dreams, akathisia, convulsion, dyskinesia, dystonia, euphoria, extrapyramidal syndrome, and twitching; Rare:withdrawal syndrome.

Respiratory System– Infrequent:epistaxis. Rare:hemoptysis and laryngismus.

Skin– Infrequent:urticaria.

Urogenital System*– Infrequent:hematuria, menorrhagia, and vaginal hemorrhage; Rare:hematospermia.

* Based on the number of males or females, as appropriate.

6.9 Postmarketing Reports

The following adverse reactions have been identified during post-approval use of Fluvoxamine Maleate Tablets. Because these reactions are reported voluntarily from a population of uncertain size, it is not always possible to reliably estimate their frequency or establish a causal relationship to drug exposure.

Voluntary reports of adverse reactions in patients taking Fluvoxamine Maleate Tablets that have been received since market introduction and are of unknown causal relationship to Fluvoxamine Maleate Tablets use include: acute renal failure, agranulocytosis, amenorrhea, anaphylactic reaction, angioedema, anosmia, aplastic anemia, bullous eruption, Henoch-Schoenlein purpura, hepatitis, hyposmia, ileus, pancreatitis, porphyria, Stevens-Johnson syndrome, toxic epidermal necrolysis, vasculitis, and ventricular tachycardia (including torsades de pointes).

7 DRUG INTERACTIONS

7.1 Potential Interactions with Drugs that Inhibit or are Metabolized by Cytochrome P450 Isoenzymes

Multiple hepatic cytochrome P450 isoenzymes are involved in the oxidative biotransformation of a large number of structurally different drugs and endogenous compounds. The available knowledge concerning the relationship of fluvoxamine and the cytochrome P450 isoenzyme system has been obtained mostly from pharmacokinetic interaction studies conducted in healthy volunteers, but some preliminary in vitrodata are also available. Based on a finding of substantial interactions of fluvoxamine with certain of these drugs [see later parts of this section and also Warnings and Precautions (5) ] and limited in vitrodata for CYP3A4, it appears that fluvoxamine inhibits several cytochrome P450 isoenzymes that are known to be involved in the metabolism of other drugs such as: CYP1A2 (e.g., warfarin, theophylline, propranolol, tizanidine), CYP2C9 (e.g., warfarin), CYP3A4 (e.g., alprazolam), and CYP2C19 (e.g., omeprazole).

In vitrodata suggest that fluvoxamine is a relatively weak inhibitor of CYP2D6.

Approximately 7% of the normal population has a genetic code that leads to reduced levels of activity of CYP2D6. Such individuals have been referred to as "poor metabolizers" (PM) of drugs such as debrisoquin, dextromethorphan, and tricyclic antidepressants. While none of the drugs studied for drug interactions significantly affected the pharmacokinetics of fluvoxamine, an in vivostudy of fluvoxamine single-dose pharmacokinetics in 13 PM subjects demonstrated altered pharmacokinetic properties compared to 16 "extensive metabolizers" (EM): mean Cmax, AUC, and half-life were increased by 52%, 200%, and 62%, respectively, in the PM compared to the EM group. This suggests that fluvoxamine is metabolized, at least in part, by CYP2D6. Caution is indicated in patients known to have reduced levels of CYP2D6 activity and those receiving concomitant drugs known to inhibit this cytochrome P450 isoenzyme (e.g., quinidine).

The metabolism of fluvoxamine has not been fully characterized and the effects of potent cytochrome P450 isoenzyme inhibition, such as the ketoconazole inhibition of CYP3A4, on fluvoxamine metabolism have not been studied.

A clinically significant fluvoxamine interaction is possible with drugs having a narrow therapeutic ratio such as pimozide, warfarin, theophylline, certain benzodiazepines, omeprazole and phenytoin. If Fluvoxamine Maleate Tablets are to be administered together with a drug that is eliminated via oxidative metabolism and has a narrow therapeutic window, plasma levels and/or pharmacodynamic effects of the latter drug should be monitored closely, at least until steady-state conditions are reached [see Contraindications (4), Warnings and Precautions (5)] .

7.2 CNS Active Drugs

Antipsychotics:See Warnings and Precautions (5.2) .

Benzodiazepines:See Warnings and Precautions (5.8) .

Alprazolam:See Warnings and Precautions (5.8) .

Diazepam:See Warnings and Precautions (5.8) .

Lorazepam:A study of multiple doses of fluvoxamine maleate (50 mg b.i.d.) in healthy male volunteers (N=12) and a single dose of lorazepam (4 mg single dose) indicated no significant pharmacokinetic interaction. On average, both lorazepam alone and lorazepam with fluvoxamine produced substantial decrements in cognitive functioning; however, the coadministration of fluvoxamine and lorazepam did not produce larger mean decrements compared to lorazepam alone.

Alcohol:Studies involving single 40 g doses of ethanol (oral administration in one study and intravenous in the other) and multiple dosing with fluvoxamine maleate (50 mg b.i.d.) revealed no effect of either drug on the pharmacokinetics or pharmacodynamics of the other. As with other psychotropic medications, patients should be advised to avoid alcohol while taking Fluvoxamine Maleate Tablets.

Carbamazepine:Elevated carbamazepine levels and symptoms of toxicity have been reported with the coadministration of fluvoxamine maleate and carbamazepine.

Clozapine:See Warnings and Precautions (5.8) .

Lithium:As with other serotonergic drugs, lithium may enhance the serotonergic effects of fluvoxamine and, therefore, the combination should be used with caution. Seizures have been reported with the coadministration of fluvoxamine maleate and lithium.

Methadone:See Warnings and Precautions (5.8) .

Monoamine Oxidase Inhibitors:See Dosage and Administration (2.4,2.5), Contraindications (4), Warnings and Precautions (5.2) .

Pimozide:See Contraindications (4), Warnings and Precautions (5.6) .

Ramelteon:See Warnings and Precautions (5.8) .

Other Serotonergic Drugs:The concomitant use of serotonergic drugs (including other SSRIs, SNRIs, triptans, tricyclic antidepressants, opioids, lithium, buspirone, amphetamines, tryptophan, and St. John's Wort) with Fluvoxamine Maleate Tablets increases the risk of serotonin syndrome. Monitor patients for signs and symptoms of serotonin syndrome, particularly during treatment initiation and dosage increases. If serotonin syndrome occurs, consider discontinuation of Fluvoxamine Maleate Tablets and/or concomitant serotonergic drugs [see Warnings and Precautions (5.2)] .

Tacrine:In a study of 13 healthy, male volunteers, a single 40 mg dose of tacrine added to fluvoxamine 100 mg/day administered at steady-state was associated with five- and eight-fold increases in tacrine Cmaxand AUC, respectively, compared to the administration of tacrine alone. Five subjects experienced nausea, vomiting, sweating, and diarrhea following coadministration, consistent with the cholinergic effects of tacrine.

Thioridazine:See Contraindications (4), Warnings and Precautions (5.4) .

Tizanidine:See Contraindications (4), Warnings and Precautions (5.5) .

Tricyclic Antidepressants (TCAs):Significantly increased plasma TCA levels have been reported with the coadministration of fluvoxamine maleate and amitriptyline, clomipramine or imipramine. Caution is indicated with the coadministration of Fluvoxamine Maleate Tablets and TCAs; plasma TCA concentrations may need to be monitored, and the dose of TCA may need to be reduced.

Triptans:There have been rare postmarketing reports of serotonin syndrome with use of an SSRI and a triptan. If concomitant treatment of fluvoxamine with a triptan is clinically warranted, careful observation of the patient is advised, particularly during treatment initiation and dose increases [see Warnings and Precautions (5.2)] .

Sumatriptan:There have been rare postmarketing reports describing patients with weakness, hyperreflexia, and incoordination following the use of a selective serotonin reuptake inhibitor (SSRI) and sumatriptan. If concomitant treatment with sumatriptan and an SSRI (e.g., fluoxetine, fluvoxamine, paroxetine, sertraline) is clinically warranted, appropriate observation of the patient is advised.

Tryptophan:Tryptophan may enhance the serotonergic effects of fluvoxamine, and the combination should, therefore, be used with caution. Severe vomiting has been reported with the coadministration of fluvoxamine maleate and tryptophan [see Warnings and Precautions (5.2)] .

7.3 Other Drugs

Alosetron:See Contraindications (4), Warnings and Precautions (5.7) , and LotronexTM(alosetron) package insert.

Digoxin:Administration of fluvoxamine maleate 100 mg daily for 18 days (N=8) did not significantly affect the pharmacokinetics of a 1.25 mg single intravenous dose of digoxin.

Diltiazem:Bradycardia has been reported with the coadministration of fluvoxamine maleate and diltiazem.

Mexiletine:See Warnings and Precautions (5.8) .

Propranolol and Other Beta-Blockers:Coadministration of fluvoxamine maleate 100 mg per day and propranolol 160 mg per day in normal volunteers resulted in a mean five-fold increase (range 2 to 17) in minimum propranolol plasma concentrations. In this study, there was a slight potentiation of the propranolol-induced reduction in heart rate and reduction in the exercise diastolic pressure.

One case of bradycardia and hypotension and a second case of orthostatic hypotension have been reported with the coadministration of fluvoxamine maleate and metoprolol.

If propranolol or metoprolol is coadministered with Fluvoxamine Maleate Tablets, a reduction in the initial beta-blocker dose and more cautious dose titration are recommended. No dosage adjustment is required for Fluvoxamine Maleate Tablets.

Coadministration of fluvoxamine maleate 100 mg per day with atenolol 100 mg per day (N=6) did not affect the plasma concentrations of atenolol. Unlike propranolol and metoprolol which undergo hepatic metabolism, atenolol is eliminated primarily by renal excretion.

Theophylline:See Warnings and Precautions (5.8) .

Warfarin and Other Drugs That Interfere With Hemostasis (NSAIDs, Aspirin, etc.):See Warnings and Precautions (5.8, 5.10) .

7.4 Effects of Smoking on Fluvoxamine Metabolism

Smokers had a 25% increase in the metabolism of fluvoxamine compared to nonsmokers.

7.5 Electroconvulsive Therapy (ECT)

There are no clinical studies establishing the benefits or risks of combined use of ECT and fluvoxamine maleate.

8 USE IN SPECIFIC POPULATIONS

8.1 Pregnancy

Pregnancy Exposure Registry

There is a pregnancy exposure registry that monitors pregnancy outcomes in women exposed to antidepressants during pregnancy. Healthcare providers are encouraged to register patients by calling the National Pregnancy Registry for Antidepressants at 1-844-405-6185 or visiting online at https://womensmentalhealth.org/clinical-and-research-programs/pregnancyregistry/antidepressants/.

Risk Summary

Based on data from published observational studies, exposure to SSRIs, particularly in the month before delivery, has been associated with a less than 2-fold increase in the risk of postpartum hemorrhage [see Warnings and Precautions (5.10) and Clinical Considerations] .

Prolonged experience with fluvoxamine in pregnant women over decades, based on published observational studies, have not identified a clear drug-associated risk of major birth defects or miscarriage (see Data). There are risks associated with untreated depression in pregnancy and risks of persistent pulmonary hypertension of the newborn (PPHN) and poor neonatal adaptation with exposure to selective serotonin reuptake inhibitors (SSRIs), including fluvoxamine, during pregnancy (see Clinical Considerations).

When pregnant rats were treated orally with fluvoxamine throughout the period of organogenesis, increased embryofetal death and increased incidences of fetal eye abnormalities (folded retinas) was observed at doses ≥3 times the maximum recommended human dose (MRHD) of 300 mg/day given to adolescents on a mg/m^2basis. In addition, decreased fetal body weight was seen at a dose 6 times the MRHD given to adolescents on a mg/m^2basis. There were no adverse developmental effects in rabbits treated with fluvoxamine during the period of organogenesis up to a dose 2 times the MRHD given to adolescents on a mg/m^2basis. When fluvoxamine was administered orally to rats during pregnancy and lactation, increased pup mortality at birth was seen at a dose 2 times the MRHD given to adolescents on a mg/m^2basis. In addition, decreases in pup body weight and survival were observed at doses that are ≥0.13 times the MRHD given to adolescents (see Data).

The estimated background risk of major birth defects and miscarriage for the indicated population is unknown. All pregnancies have a background risk of birth defect, loss, or other adverse outcomes. In the U.S. general population, the estimated background risks of major birth defects and miscarriage in clinically recognized pregnancies is 2 to 4% and 15 to 20%, respectively.

Clinical Considerations

Disease-associated maternal and/or embryo/fetal risk

Women who discontinue antidepressants during pregnancy are more likely to experience a relapse of major depression than women who continue antidepressants. This finding is from a prospective, longitudinal study that followed 201 pregnant women with a history of major depressive disorder who were euthymic and taking antidepressants at the beginning of pregnancy. Consider the risk of untreated depression when discontinuing or changing treatment with antidepressant medication during pregnancy and postpartum.

Maternal Adverse Reactions

Use of Fluvoxamine Maleate Tablets in the month before delivery may be associated with an increased risk of postpartum hemorrhage [see Warnings and Precautions (5.10)] .

Fetal/Neonatal adverse reactions

Neonates exposed to Fluvoxamine Maleate Tablets and other SSRIs or SNRIs late in the third trimester have developed complications requiring prolonged hospitalization, respiratory support, and tube feeding. Such complications can arise immediately upon delivery. Reported clinical findings have included respiratory distress, cyanosis, apnea, seizures, temperature instability, feeding difficulty, vomiting, hypoglycemia, hypotonia, hypertonia, hyperreflexia, tremor, jitteriness, irritability, and constant crying. These features are consistent with either a direct toxic effect of SSRIs and SNRIs or, possibly, a drug discontinuation syndrome. It should be noted that, in some cases, the clinical picture is consistent with serotonin syndrome [see Warnings and Precautions (5.2)] .

Data

Human Data

Exposure during late pregnancy to SSRIs may have an increased risk for persistent pulmonary hypertension of the newborn (PPHN). PPHN occurs in 1-2 per 1000 live births in the general population and is associated with substantial neonatal morbidity and mortality.

Animal Data

When pregnant rats were given oral doses of fluvoxamine (60, 120, or 240 mg/kg) throughout the period of organogenesis, developmental toxicity in the form of increased embryofetal death and increased incidences of fetal eye abnormalities (folded retinas) was observed at doses of 120 mg/kg or greater (3 times the MRHD of 300 mg/day, given to adolescents on a mg/m^2basis). Decreased fetal body weight was seen at the high dose of 240 mg/kg/day (6 times the MRHD given to adolescents on a mg/m^2basis). The no effect dose for developmental toxicity in this study was 60 mg/kg/day (1.6 times the MRHD given to adolescents on a mg/m^2basis).

In a study in which pregnant rabbits were administered doses of up to 40 mg/kg (approximately 2.1 times the MRHD given to adolescents on a mg/m^2basis) during the period of organogenesis, no adverse effects on embryofetal development were observed.

In other reproduction studies in which female rats were dosed orally during pregnancy and lactation (5, 20, 80, or 160 mg/kg), increased pup mortality at birth was seen at doses of 80 mg/kg/day (2 times the MRHD given to adolescents on a mg/m^2basis) or greater and decreases in pup body weight and survival were observed at all doses (low effect dose approximately 0.13 times the MRHD given to adolescents on a mg/m^2basis).

8.2 Lactation

Data from published literature report the presence of fluvoxamine is in human milk (see Data). No adverse effects on the breastfed infant have been reported in most cases of maternal use of fluvoxamine during breastfeeding. However, there are reports of diarrhea, vomiting, decreased sleep, and agitation (see Clinical Considerations). There are no data on the effect of fluvoxamine on milk production. The developmental and health benefits of breastfeeding should be considered along with the mother’s clinical need for fluvoxamine and any potential adverse effects on the breastfed child from fluvoxamine or from the underlying maternal condition.

Clinical Considerations

Monitor infants exposed to fluvoxamine through breast milk for diarrhea, vomiting, decreased sleep, and agitation.

Data

Milk drug concentrations ≤ 425 ng/mL were observed following maternal dosing of fluvoxamine 25 mg/day to 300 mg/day in published case reports and case series.

8.3 Females and Males of Reproductive Potential

Infertility

Animal findings suggest fertility may be impaired while taking fluvoxamine [see Nonclinical Toxicology (13.1)] .

8.4 Pediatric Use

The efficacy of fluvoxamine maleate for the treatment of obsessive compulsive disorder was demonstrated in a 10-week multicenter placebo controlled study with 120 outpatients ages 8-17. In addition, 99 of these outpatients continued open-label fluvoxamine maleate treatment for up to another one to three years, equivalent to 94 patient years. The adverse event profile observed in that study was generally similar to that observed in adult studies with fluvoxamine [see Adverse Reactions (6.3), Dosage and Administration (2.2)] .

Decreased appetite and weight loss have been observed in association with the use of fluvoxamine as well as other SSRIs. Consequently, regular monitoring of weight and growth is recommended if treatment of a child with an SSRI is to be continued long term.

The risks, if any, that may be associated with fluvoxamine’s extended use in children and adolescents with OCD have not been systematically assessed. The prescriber should be mindful that the evidence relied upon to conclude that fluvoxamine is safe for use in children and adolescents derives from relatively short term clinical studies and from extrapolation of experience gained with adult patients. In particular, there are no studies that directly evaluate the effects of long term fluvoxamine use on the growth, cognitive behavioral development, and maturation of children and adolescents. Although there is no affirmative finding to suggest that fluvoxamine possesses a capacity to adversely affect growth, development or maturation, the absence of such findings is not compelling evidence of the absence of the potential of fluvoxamine to have adverse effects in chronic use [see Warnings and Precautions (5.1)] .

Safety and effectiveness in the pediatric population other than pediatric patients with OCD have not been established [see Boxed Warning, Warnings and Precautions (5.1)] Anyone considering the use of Fluvoxamine Maleate Tablets in a child or adolescent must balance the potential risks with the clinical need.

8.5 Geriatric Use

Approximately 230 patients participating in controlled premarketing studies with Fluvoxamine Maleate Tablets were 65 years of age or over. No overall differences in safety were observed between these patients and younger patients. Other reported clinical experience has not identified differences in response between the elderly and younger patients. However, SSRIs and SNRIs, including Fluvoxamine Maleate Tablets, have been associated with several cases of clinically significant hyponatremia in elderly patients, who may be at greater risk for this adverse event [see Warnings and Precautions (5.13)] . Furthermore, the clearance of fluvoxamine is decreased by about 50% in elderly compared to younger patients [see Clinical Pharmacology (12.3)] , and greater sensitivity of some older individuals also cannot be ruled out. Consequently, a lower starting dose should be considered in elderly patients and Fluvoxamine Maleate Tablets should be slowly titrated during initiation of therapy.

9 DRUG ABUSE AND DEPENDENCE

9.1 Controlled Substance

Fluvoxamine Maleate Tablets are not a controlled substance.

9.3 Dependence

The potential for abuse, tolerance and physical dependence with fluvoxamine maleate has been studied in a nonhuman primate model. No evidence of dependency phenomena was found. The discontinuation effects of Fluvoxamine Maleate Tablets were not systematically evaluated in controlled clinical trials. Fluvoxamine Maleate Tablets were not systematically studied in clinical trials for potential for abuse, but there was no indication of drug-seeking behavior in clinical trials. It should be noted, however, that patients at risk for drug dependency were systematically excluded from investigational studies of fluvoxamine maleate. Generally, it is not possible to predict on the basis of preclinical or premarketing clinical experience the extent to which a CNS active drug will be misused, diverted, and/or abused once marketed. Consequently, physicians should carefully evaluate patients for a history of drug abuse and follow such patients closely, observing them for signs of fluvoxamine maleate misuse or abuse (i.e., development of tolerance, incrementation of dose, drug-seeking behavior).

10 OVERDOSAGE

The following have been reported with fluvoxamine tablet overdosage:

- Seizures, which may be delayed, and altered mental status including coma.
- Cardiovascular toxicity, which may be delayed, including QRS and QTc interval prolongation. Hypertension most commonly seen, but rarely can see hypotension alone or with co-ingestants including alcohol.
- Serotonin syndrome (patients with a multiple drug overdosage with other pro-serotonergic drugs may have a higher risk).

Gastrointestinal decontamination with activated charcoal should be considered in patients who present early after a fluvoxamine overdose.

Consider contacting a poison center (1-800-221-2222) or a medical toxicologist for overdosage management recommendations.

11 DESCRIPTION

Fluvoxamine maleate is a selective serotonin (5-HT) reuptake inhibitor (SSRI) belonging to the chemical series, the 2-aminoethyl oxime ethers of aralkylketones.

It is chemically designated as 5-methoxy-4′-(trifluoromethyl)valerophenone-(E)-O-(2-aminoethyl)oxime maleate (1:1) and has the empirical formula C15H21O2N2F3∙C4H4O4. Its molecular weight is 434.41.

The structural formula is:

Fluvoxamine maleate is a white to off white, odorless, crystalline powder which is sparingly soluble in water, freely soluble in ethanol and chloroform and practically insoluble in diethyl ether.

Fluvoxamine Maleate Tablets are available in 25 mg, 50 mg and 100 mg strengths for oral administration. In addition to the active ingredient, fluvoxamine maleate, each tablet contains the following inactive ingredients: mannitol, polyethylene glycol, polyvinyl alcohol, pregelatinized starch (potato), silicon dioxide, sodium stearyl fumarate, starch (corn), talc, and titanium dioxide. The 50 mg and 100 mg tablets also contain synthetic iron oxides.

12 CLINICAL PHARMACOLOGY

12.1 Mechanism of Action

The mechanism of action of fluvoxamine maleate in obsessive compulsive disorder is presumed to be linked to its specific serotonin reuptake inhibition in brain neurons. Fluvoxamine has been shown to be a potent inhibitor of the serotonin reuptake transporter in preclinical studies, both in vitroand in vivo.

12.2 Pharmacodynamics

In in vitrostudies, fluvoxamine maleate had no significant affinity for histaminergic, alpha or beta adrenergic, muscarinic, or dopaminergic receptors. Antagonism of some of these receptors is thought to be associated with various sedative, cardiovascular, anticholinergic, and extrapyramidal effects of some psychotropic drugs.

12.3 Pharmacokinetics

Absorption:The absolute bioavailability of fluvoxamine maleate is 53%. Oral bioavailability is not significantly affected by food.

In a dose proportionality study involving fluvoxamine maleate at 100, 200 and 300 mg/day for 10 consecutive days in 30 normal volunteers, steady state was achieved after about a week of dosing. Maximum plasma concentrations at steady state occurred within 3 to 8 hours of dosing and reached concentrations averaging 88, 283 and 546 ng/mL, respectively. Thus, fluvoxamine had nonlinear pharmacokinetics over this dose range, i.e., higher doses of fluvoxamine maleate produced disproportionately higher concentrations than predicted from the lower dose.

Distribution:The mean apparent volume of distribution for fluvoxamine is approximately 25 L/kg, suggesting extensive tissue distribution.

Approximately 80% of fluvoxamine is bound to plasma protein, mostly albumin, over a concentration range of 20 to 2000 ng/mL.

Metabolism:Fluvoxamine maleate is extensively metabolized by the liver; the main metabolic routes are oxidative demethylation and deamination. Nine metabolites were identified following a 5 mg radiolabelled dose of fluvoxamine maleate, constituting approximately 85% of the urinary excretion products of fluvoxamine. The main human metabolite was fluvoxamine acid which, together with its N-acetylated analog, accounted for about 60% of the urinary excretion products. A third metabolite, fluvoxethanol, formed by oxidative deamination, accounted for about 10%. Fluvoxamine acid and fluvoxethanol were tested in an in vitroassay of serotonin and norepinephrine reuptake inhibition in rats; they were inactive except for a weak effect of the former metabolite on inhibition of serotonin uptake (1-2 orders of magnitude less potent than the parent compound). Approximately 2% of fluvoxamine was excreted in urine unchanged [see Drug Interactions (7)] .

Elimination:Following a^14C-labelled oral dose of fluvoxamine maleate (5 mg), an average of 94% of drug-related products was recovered in the urine within 71 hours.

The mean plasma half-life of fluvoxamine at steady state after multiple oral doses of 100 mg/day in healthy, young volunteers was 15.6 hours.

Elderly Subjects:In a study of Fluvoxamine Maleate Tablets at 50 and 100 mg comparing elderly (ages 66-73) and young subjects (ages 19-35), mean maximum plasma concentrations in the elderly were 40% higher. The multiple dose elimination half-life of fluvoxamine was 17.4 and 25.9 hours in the elderly compared to 13.6 and 15.6 hours in the young subjects at steady state for 50 and 100 mg doses, respectively. In elderly patients, the clearance of fluvoxamine was reduced by about 50% and, therefore, Fluvoxamine Maleate Tablets should be slowly titrated during initiation of therapy [see Dosage and Administration (2.3)] .

Pediatric Subjects:The multiple-dose pharmacokinetics of fluvoxamine were determined in male and female children (ages 6-11) and adolescents (ages 12-17). Steady-state plasma fluvoxamine concentrations were 2-3 fold higher in children than in adolescents. AUC and Cmaxin children were 1.5- to 2.7-fold higher than that in adolescents. (See Table 4.) As in adults, both children and adolescents exhibited nonlinear multiple-dose pharmacokinetics. Female children showed significantly higher AUC (0-12) and Cmaxcompared to male children and, therefore, lower doses of Fluvoxamine Maleate Tablets may produce therapeutic benefit. (See Table 5.) No gender differences were observed in adolescents. Steady-state plasma fluvoxamine concentrations were similar in adults and adolescents at a dose of 300 mg/day, indicating that fluvoxamine exposure was similar in these two populations. (See Table 4.) Dose adjustment in adolescents (up to the adult maximum dose of 300 mg) may be indicated to achieve therapeutic benefit [see Dosage and Administration (2.2)] .

TABLE 4 COMPARISON OF MEAN (SD) FLUVOXAMINE PHARMACOKINETIC PARAMETERS BETWEEN CHILDREN, ADOLESCENTS, AND ADULTS
Pharmacokinetic Parameter; (body weight corrected) | Dose = 200 mg/day; (100 mg b.i.d.) |  | Dose = 300 mg/day; (150 mg b.i.d.)
Pharmacokinetic Parameter; (body weight corrected) | Children; (N=10) | Adolescent; (N=17) | Adolescent; (N=13) | Adult; (N=16)
AUC 0-12 (ng .h/mL/kg) | 155.1 (160.9) | 43.9 (27.9) | 69.6 (46.6) | 59.4 (40.9)
Cmax(ng/mL/kg) | 14.8 (14.9) | 4.2 (2.6) | 6.7 (4.2) | 5.7 (3.9)
Cmin(ng/mL/kg) | 11.0 (11.9) | 2.9 (2.0) | 4.8 (3.8) | 4.6 (3.2)

TABLE 5 COMPARISON OF MEAN (SD) FLUVOXAMINE PHARMACOKINETIC PARAMETERS BETWEEN MALE AND FEMALE CHILDREN (6-11 YEARS)
Pharmacokinetic Parameter; (body weight corrected) | Dose = 200 mg/day (100 mg b.i.d.)
Pharmacokinetic Parameter; (body weight corrected) | Male Children; (N=7) | Female Children; (N=3)
AUC 0-12 (ng .h/mL/kg) | 95.8 (83.9) | 293.5 (233.0)
Cmax(ng/mL/kg) | 9.1 (7.6) | 28.1 (21.1)
Cmin(ng/mL/kg) | 6.6 (6.1) | 21.2 (17.6)

Hepatic and Renal Disease:A cross study comparison (healthy subjects versus patients with hepatic dysfunction) suggested a 30% decrease in fluvoxamine clearance in association with hepatic dysfunction. The mean minimum plasma concentrations in renally impaired patients (creatinine clearance of 5 to 45 mL/min) after 4 and 6 weeks of treatment (50 mg b.i.d., N=13) were comparable to each other, suggesting no accumulation of fluvoxamine in these patients [see Warnings and Precautions (5.14)] .

13 NONCLINICAL TOXICOLOGY

13.1 Carcinogenesis, Mutagenesis, Impairment of Fertility

Carcinogenesis:There was no evidence of carcinogenicity in rats treated orally with fluvoxamine maleate for 30 months or hamsters treated orally with fluvoxamine maleate for 20 (females) or 26 (males) months. The daily doses in the high dose groups in these studies were increased over the course of the study from a minimum of 160 mg/kg to a maximum of 240 mg/kg in rats, and from a minimum of 135 mg/kg to a maximum of 240 mg/kg in hamsters. The maximum dose of 240 mg/kg is approximately 5 and 6 times, respectively (in hamsters and rats), the MRHD given to children on a mg/m^2basis.

Mutagenesis:No evidence of genotoxic potential was observed in a mouse micronucleus test, an in vitrochromosome aberration test, or the Ames microbial mutagen test with or without metabolic activation.

Impairment of Fertility:In a study in which male and female rats were administered fluvoxamine (60, 120, or 240 mg/kg) prior to and during mating and gestation, fertility was impaired at oral doses of 120 mg/kg (3 times the MRHD given to adolescents on a mg/m^2basis) or greater, as evidenced by increased latency to mating, decreased sperm count, decreased epididymal weight, and decreased pregnancy rate. In addition, the numbers of implantations and embryos were decreased at the highest dose (6 times the MRHD in adolescents on a mg/m^2basis). The no effect dose for fertility impairment was 60 mg/kg (1.6 times the MRHD given to adolescents on a mg/m^2basis).

14 CLINICAL STUDIES

14.1 Adult OCD Studies

The effectiveness of Fluvoxamine Maleate Tablets for the treatment of obsessive compulsive disorder (OCD) was demonstrated in two 10-week multicenter, parallel group studies of adult outpatients. Patients in these trials were titrated to a total daily fluvoxamine maleate dose of 150 mg/day over the first two weeks of the trial, following which the dose was adjusted within a range of 100-300 mg/day (on a b.i.d. schedule), on the basis of response and tolerance. Patients in these studies had moderate to severe OCD (DSM-III-R), with mean baseline ratings on the Yale-Brown Obsessive Compulsive Scale (Y-BOCS), total score of 23. Patients receiving fluvoxamine maleate experienced mean reductions of approximately 4 to 5 units on the Y-BOCS total score, compared to a 2 unit reduction for placebo patients.

Table 6provides the outcome classification by treatment group on the Global Improvement item of the Clinical Global Impressions (CGI) scale for both studies combined.

TABLE 6 OUTCOME CLASSIFICATION (%) ON CGI-GLOBAL IMPROVEMENT ITEM FOR COMPLETERS IN POOL OF TWO ADULT OCD STUDIES
Outcome Classification | Fluvoxamine (N=120) | Placebo (N=134)
Very Much Improved | 13% | 2%
Much Improved | 30% | 10%
Minimally Improved | 22% | 32%
No Change | 31% | 51%
Worse | 4% | 6%

Exploratory analyses for age and gender effects on outcomes did not suggest any differential responsiveness on the basis of age or sex.

14.2 Adult OCD Maintenance Study

In a maintenance trial of adult outpatients with OCD, 114 patients meeting DSM-IV criteria for OCD and with a Yale-Brown Obsessive Compulsive Scale (Y-BOCS) score ≥18 were titrated to an effective dose of Fluvoxamine Maleate Tablets 100 to 300 mg/day as part of an initial 10-week single-blind treatment phase. Treatment response during this single-blind phase was defined as Y-BOCS scores at least 30% lower than baseline at the end of weeks 8 and 10. Of the patients who responded, their average duration of response was 4 weeks. Patients who responded during this initial phase were randomized either to continuation of Fluvoxamine Maleate Tablets (N=56) or to placebo (N=58) in a double-blind phase for observation of relapse. Relapse during the double-blind phase was defined as an increase in the Y-BOCS score of at least 30% over the baseline for that phase or patient refusal to continue treatment due to a substantial increase in OCD symptoms. In the double-blind phase, patients receiving continued Fluvoxamine Maleate Tablets treatment experienced, on average, a significantly lower relapse rate than those receiving placebo.

An examination of population subgroups from this trial did not reveal any clear evidence of a differential maintenance effect on the basis of age or gender.

14.3 Pediatric OCD Study

The effectiveness of Fluvoxamine Maleate Tablets for the treatment of OCD was also demonstrated in a 10-week multicenter, parallel group study in a pediatric outpatient population (children and adolescents, ages 8-17). Patients in this study were titrated to a total daily fluvoxamine dose of approximately 100 mg/day over the first two weeks of the trial, following which the dose was adjusted within a range of 50-200 mg/day (on a b.i.d. schedule) on the basis of response and tolerance. All patients had moderate to severe OCD (DSM-III-R) with mean baseline ratings on the Children’s Yale-Brown Obsessive Compulsive Scale (CY-BOCS) total score of 24. Patients receiving fluvoxamine maleate experienced mean reductions of approximately six units on the CY-BOCS total score, compared to a three-unit reduction for placebo patients.

Table 7provides the outcome classification by treatment group on the Global Improvement item of the Clinical Global Impression (CGI) scale for the pediatric study.

TABLE 7 OUTCOME CLASSIFICATION (%) ON CGI-GLOBAL IMPROVEMENT ITEM FOR COMPLETERS IN PEDIATRIC STUDY
Outcome Classification | Fluvoxamine (N=38) | Placebo (N=36)
Very Much Improved | 21% | 11%
Much Improved | 18% | 17%
Minimally Improved | 37% | 22%
No Change | 16% | 44%
Worse | 8% | 6%

Post hoc exploratory analyses for gender effects on outcomes did not suggest any differential responsiveness on the basis of gender. Further exploratory analyses revealed a prominent treatment effect in the 8-11 age group and essentially no effect in the 12-17 age group. While the significance of these results is not clear, the 2-3 fold higher steady-state plasma fluvoxamine concentrations in children compared to adolescents [see Clinical Pharmacology (12.3)] is suggestive that decreased exposure in adolescents may have been a factor, and dose adjustment in adolescents (up to the adult maximum dose of 300 mg) may be indicated to achieve therapeutic benefit.

16 HOW SUPPLIED/STORAGE AND HANDLING

Fluvoxamine Maleate Tablets USP are available in the following strengths, colors, imprints, and presentation:

Tablets 50 mg: scored, yellow, elliptical, film-coated (debossed “1225” on one side and scored on the other)

NDC: 70518-1643-00

PACKAGING: 30 in 1 BLISTER PACK

Keep out of reach of children.

Fluvoxamine Maleate Tablets should be protected from high humidity and stored at 20° to 25°C (68° to 77°F); excursions permitted to 15° to 30°C (59° to 86°F) [see USP Controlled Room Temperature].

Dispense in tight containers.

Repackaged and Distributed By:

Remedy Repack, Inc.

625 Kolter Dr. Suite #4 Indiana, PA 1-724-465-8762

17 PATIENT COUNSELING INFORMATION

Advise the patient to read the FDA-approved patient labeling (Medication Guide).

Prescribers or other health professionals should inform patients, their families, and their caregivers about the benefits and risks associated with treatment with Fluvoxamine Maleate Tablets and should counsel them in the appropriate use. A patient Medication Guide about “Antidepressant Medicines, Depression and other Serious Mental Illnesses, and Suicidal Thoughts or Actions” is available for Fluvoxamine Maleate Tablets. The prescriber or health professional should instruct patients, their families, and their caregivers to read the Medication Guide and should assist them in understanding its contents. Patients should be given the opportunity to discuss the contents of the Medication Guide and to obtain answers to any questions they may have. The complete text of the Medication Guide is reprinted at the end of this document.

Patients should be advised of the following issues and asked to alert their prescriber if these occur while taking Fluvoxamine Maleate Tablets.

Clinical Worsening and Suicide Risk

Patients, their families, and their caregivers should be encouraged to be alert to the emergence of anxiety, agitation, panic attacks, insomnia, irritability, hostility, aggressiveness, impulsivity, akathisia (psychomotor restlessness), hypomania, mania, other unusual changes in behavior, worsening of depression, and suicidal ideation, especially early during antidepressant treatment and when the dose is adjusted up or down. Families and caregivers of patients should be advised to look for the emergence of such symptoms on a day-to-day basis, since changes may be abrupt. Such symptoms should be reported to the patient’s prescriber or health professional, especially if they are severe, abrupt in onset, or were not part of the patient’s presenting symptoms. Symptoms such as these may be associated with an increased risk for suicidal thinking and behavior and indicate the need for very close monitoring and possibly changes in the medication [see Boxed Warning, Warnings and Precautions (5.1)] .

Serotonin Syndrome

Patients should be cautioned about the risk of serotonin syndrome particularly with the concomitant use of fluvoxamine with other serotonergic agents (including triptans, tricyclic antidepressants, opioids, lithium, tryptophan, buspirone, amphetamines, and St. John's Wort) [see Warnings and Precautions (5.2)] .

Angle Closure Glaucoma

Patients should be advised that taking Fluvoxamine Maleate Tablets can cause mild pupillary dilation, which in susceptible individuals, can lead to an episode of angle closure glaucoma. Pre-existing glaucoma is almost always open-angle glaucoma because angle closure glaucoma, when diagnosed, can be treated definitively with iridectomy. Open-angle glaucoma is not a risk factor for angle closure glaucoma. Patients may wish to be examined to determine whether they are susceptible to angle closure, and have a prophylactic procedure (e.g., iridectomy), if they are susceptible [see Warnings and Precautions (5.3)] .

Interference with Cognitive or Motor Performance

Since any psychoactive drug may impair judgment, thinking, or motor skills, patients should be cautioned about operating hazardous machinery, including automobiles, until they are certain that Fluvoxamine Maleate Tablets therapy does not adversely affect their ability to engage in such activities.

Pregnancy

- Advise pregnant women to notify their healthcare provider if they become pregnant or intend to become pregnant during treatment with Fluvoxamine Maleate Tablets.
- Advise patients that Fluvoxamine Maleate Tablets use late in pregnancy may lead to an increased risk for neonatal complications requiring prolonged hospitalization, respiratory support, tube feeding, and/or persistent pulmonary hypertension of the newborn (PPHN).
- Advise women that there is a risk of relapse with discontinuation of antidepressants.
- Advise women that there is a pregnancy exposure registry that monitors pregnancy outcomes in women exposed to Fluvoxamine Maleate Tablets during pregnancy [see Use in Specific Populations (8.1)] .

Lactation

Advise breastfeeding women using Fluvoxamine Maleate Tablets to monitor infants for diarrhea, vomiting, decreased sleep, and agitation and to seek medical care if they notice these signs [see Use in Specific Populations (8.2)] .

Concomitant Medication

Patients should be advised to notify their physicians if they are taking, or plan to take, any prescription or over-the-counter drugs, since there is a potential for clinically important interactions with Fluvoxamine Maleate Tablets.

Patients should be cautioned about the concomitant use of fluvoxamine and NSAIDs, aspirin, or other drugs that affect coagulation since the combined use of psychotropic drugs that interfere with serotonin reuptake and these agents has been associated with an increased risk of bleeding [see Warnings and Precautions (5.8)] .

Because of the potential for the increased risk of serious adverse reactions including severe lowering of blood pressure and sedation when fluvoxamine and tizanidine are used together, fluvoxamine should not be used with tizanidine [see Warnings and Precautions (5.5)] .

Because of the potential for the increased risk of serious adverse reactions when fluvoxamine and alosetron are used together, fluvoxamine should not be used with LotronexTM(alosetron) [see Warnings and Precautions (5.7)] .

Sexual Dysfunction

Advise patients that use of Fluvoxamine Maleate Tablets may cause symptoms of sexual dysfunction in both male and female patients. Inform patients that they should discuss any changes in sexual function and potential management strategies with their healthcare provider [see Warnings and Precautions (5.16)] .

Alcohol

As with other psychotropic medications, patients should be advised to avoid alcohol while taking Fluvoxamine Maleate Tablets.

Allergic Reactions

Patients should be advised to notify their physicians if they develop a rash, hives, or a related allergic phenomenon during therapy with Fluvoxamine Maleate Tablets.

All brand names listed are the registered trademarks of their respective owners and are not trademarks of ANI Pharmaceuticals, Inc.

Repackaged By / Distributed By: RemedyRepack Inc.

625 Kolter Drive, Indiana, PA 15701

(724) 465-8762

MEDICATION GUIDE

Fluvoxamine (Flu VOX ah meen) Maleate Tablets

Read the Medication Guide that comes with Fluvoxamine Maleate Tablets before you start taking it and each time you get a refill. There may be new information. This Medication Guide does not take the place of talking to your healthcare provider about your medical condition or treatment. Talk with your healthcare provider if there is something you do not understand or want to learn more about.

What is the most important information I should know about Fluvoxamine Maleate Tablets?

Fluvoxamine is the same kind of medicine as those used to treat depression and may cause serious side effects, including:

1. Suicidal thoughts or actions:

- Fluvoxamine Maleate Tablets and antidepressant medicines may increase suicidal thoughts or actionsin some children, teenagers, or young adults within the first few months of treatment or when the dose is changed.
- Depression or other serious mental illnesses are the most important causes of suicidal thoughts or actions.
- Watch for these changes and call your healthcare provider right away if you notice:
  - New or sudden changes in mood, behavior, actions, thoughts, or feelings, especially if severe.
  - Pay particular attention to such changes when Fluvoxamine Maleate Tablets is started or when the dose is changed.
- Keep all follow-up visits with your healthcare provider and call between visits if you are worried about symptoms.

Call your healthcare provider right away if you have any of the following symptoms, or call 911 if an emergency, especially if they are new, worse, or worry you:

- attempts to commit suicide
- acting on dangerous impulses
- acting aggressive or violent
- thoughts about suicide or dying
- new or worse depression
- new or worse anxiety or panic attacks
- feeling agitated, restless, angry or irritable
- trouble sleeping
- an increase in activity or talking more than what is normal for you
- other unusual changes in behavior or mood

Tell your healthcare provider right away if you have any of the following symptoms, or call 911 if an emergency. Fluvoxamine Maleate Tablets may be associated with these serious side effects:

2. Serotonin Syndrome: This condition can be life-threatening and may include:

- agitation, hallucinations, coma or other changes in mental status
- coordination problems or muscle twitching (overactive reflexes)
- racing heartbeat, high or low blood pressure
- sweating or fever
- nausea, vomiting, or diarrhea
- muscle rigidity

3. Visual problems

- eye pain
- changes in vision
- swelling or redness in or around the eye

Only some people are at risk for these problems. You may want to undergo an eye examination to see if you are at risk and receive preventative treatment if you are.

4. Severe allergic reactions:

- trouble breathing
- swelling of the face, tongue, eyes, or mouth
- rash, itchy welts (hives) or blisters, alone or with fever or joint pain

5. Abnormal bleeding:Fluvoxamine Maleate Tablets and antidepressant medicines may increase your risk of bleeding or bruising, especially if you take the blood thinner warfarin (Coumadin®, Jantoven®), or a non-steroidal anti-inflammatory drug (NSAIDs, like ibuprofen, naproxen, or aspirin).

6. Seizures or convulsions

7. Manic episodes:

- greatly increased energy
- severe trouble sleeping
- racing thoughts
- reckless behavior
- unusually grand ideas
- excessive happiness or irritability
- talking more or faster than usual

8. Changes in appetite or weight.Children and adolescents should have height and weight monitored during treatment.

9. Low salt (sodium) levels in the blood.Elderly people may be at greater risk for this. Symptoms may include:

- headache
- weakness or feeling unsteady
- confusion, problems concentrating or thinking or memory problems

10. Sexual problems (dysfunction).Taking selective serotonin reuptake inhibitors (SSRIs), including Fluvoxamine Maleate Tablets, may cause sexual problems.

- Symptoms in males may include:
  - Delayed ejaculation or inability to have an ejaculation
  - Decreased sex drive
  - Problems getting or keeping an erection
- Symptoms in females may include:
  - Decreased sex drive
  - Delayed orgasm or inability to have an orgasm

Talk to your healthcare provider if you develop any changes in your sexual function or if you have any questions or concerns about sexual problems during treatment with Fluvoxamine Maleate Tablets. There may be treatments your healthcare provider can suggest.

Do not stop Fluvoxamine Maleate Tablets without first talking to your healthcare provider.

Stopping Fluvoxamine Maleate Tablets too quickly may cause serious symptoms including:

- anxiety, irritability, high or low mood, feeling restless or changes in sleep habits
- headache, sweating, nausea, dizziness
- electric shock-like sensations, shaking, confusion

What are Fluvoxamine Maleate Tablets?

Fluvoxamine Maleate Tablets are a prescription medicine used to treat obsessive compulsive disorder (OCD). It is important to talk with your healthcare provider about the risks of treating OCD and also the risks of not treating it. You should discuss all treatment choices with your healthcare provider.

Talk to your healthcare provider if you do not think that your condition is getting better with Fluvoxamine Maleate Tablets treatment.

Who should not take Fluvoxamine Maleate Tablets?

Do not take Fluvoxamine Maleate Tablets if you:

- are allergic to fluvoxamine maleate or any of the ingredients in Fluvoxamine Maleate Tablets. See the end of this Medication Guide for a complete list of ingredients in Fluvoxamine Maleate Tablets.
- take a Monoamine Oxidase Inhibitor (MAOI). Ask your healthcare provider or pharmacist if you are not sure if you take an MAOI, including the antibiotic linezolid.
  - Do not take an MAOI within 2 weeks of stopping Fluvoxamine Maleate Tablets unless directed to do so by your physician.
  - Do not start Fluvoxamine Maleate Tablets if you stopped taking an MAOI in the last 2 weeks unless directed to do so by your physician.
    People who take Fluvoxamine Maleate Tablets close in time to an MAOI may have serious or even life-threatening side effects. Get medical help right away if you have any of these symptoms:
  - high fever
  - uncontrolled muscle spasms
  - stiff muscles
  - rapid changes in heart rate or blood pressure
  - confusion
  - loss of consciousness (pass out)
- take Mellaril®(thioridazine). Do not take Mellaril®within 2 weeks of stopping Fluvoxamine Maleate Tablets because this can cause serious heart rhythm problems or sudden death.
- take Orap®(pimozide) because taking this drug with Fluvoxamine Maleate Tablets can cause serious heart rhythm problems or sudden death.
- take Zanaflex®(tizanidine). Fluvoxamine Maleate Tablets could increase the amount of Zanaflex in your body, which could increase its actions and side effects. This could include drowsiness and a drop in blood pressure and affecting how well you do things that require alertness.
- Take Lotronex®(alosetron). Fluvoxamine Maleate Tablets may increase the amount of Lotronex in your body, which could increase its actions and side effects.

What should I tell my healthcare provider before taking Fluvoxamine Maleate Tablets? Ask if you are not sure.
Before starting Fluvoxamine Maleate Tablets, tell your healthcare provider if you:

- Are taking certain drugs such as:
  - Monoamine oxidase inhibitors (MAOIs) such as Emsam®(selegiline), Nardil®(phenelzine), or Parnate®(tranylcypromine)
  - Mellaril® (thioridazine): used to treat mental or mood problems
  - Zanaflex®(tizanidine): used to treat spasticity (a condition in which muscles keep tightening and cramping)
  - Orap®(pimozide): used to treat Tourette Syndrome (a brain condition causing tics)
  - Lotronex®(alosetron): used to treat a condition with diarrhea, continuing stomach pain, cramps, and bloating
  - Triptans: used to treat migraine headache
  - Medicines used to treat mood, anxiety, psychotic or thought disorders, including tricyclics, lithium, SSRIs, SNRIs, or antipsychotics
  - Tramadol, fentanyl, meperidine, methadone, or other opioids
  - Benzodiazepines: used to reduce anxiety, stress, emotional upset, or seizures; helps you sleep; helps with alcohol withdrawal; reduces restlessness; and relaxes muscles
  - Clozapine: used to treat mental disorders
  - Mexiletine: used to treat abnormalities in heart rhythm
  - Theophylline: used to treat swollen air passages in your lungs, to relax the muscles in your chest to ease shortness of breath, often to treat asthma
  - Warfarin and other drugs that affect how your blood clots
  - Diuretics to treat high blood pressure, congestive heart failure, or swelling
  - Over-the-counter supplements such as tryptophan or St. John’s Wort
- have liver problems
- have kidney problems
- have heart problems
- have or had seizures or convulsions
- have bipolar disorder or mania
- have low sodium levels in your blood
- have a history of a stroke
- have high blood pressure
- have or had bleeding problems
- are pregnant or plan to become pregnant. Talk to your healthcare provider about the risk to your unborn baby if you take Fluvoxamine Maleate Tablets.
  - Talk to your healthcare provider about the benefits and risks of treating OCD during pregnancy.
  - If you become pregnant during treatment with Fluvoxamine Maleate Tablets, talk to your healthcare provider about registering with the National Pregnancy Registry for Antidepressants. You can register by calling 1-844-405-6185.
- are breast-feeding or plan to breast-feed. Fluvoxamine Maleate Tablets pass into your breast milk. Talk to your healthcare provider about the best way to feed your baby while taking Fluvoxamine Maleate Tablets.

Tell your healthcare provider about all the medicines that you take,including prescription and non-prescription medicines, vitamins, and herbal supplements. Fluvoxamine Maleate Tablets and some medicines may interact with each other, may not work as well, or may cause serious side effects.

Your healthcare provider or pharmacist can tell you if it is safe to take Fluvoxamine Maleate Tablets with your other medicines. Do not start or stop any medicine while taking Fluvoxamine Maleate Tablets without talking to your healthcare provider first.

Repackaged By / Distributed By: RemedyRepack Inc.

625 Kolter Drive, Indiana, PA 15701

(724) 465-8762

BOXED WARNING

If you take Fluvoxamine Maleate Tablets, you should not take any other medicines that contain fluvoxamine including: LUVOX CR®

How should I take Fluvoxamine Maleate Tablets?

- Take Fluvoxamine Maleate Tablets exactly as prescribed. Your healthcare provider may need to change the dose of Fluvoxamine Maleate Tablets until it is the right dose for you.
- Fluvoxamine Maleate Tablets may be taken with or without food.
- If you miss a dose of Fluvoxamine Maleate Tablets, take the missed dose as soon as you remember. If it is almost time for the next dose, skip the missed dose and take your next dose at the regular time. Do not take two doses of Fluvoxamine Maleate Tablets at the same time.
- If you take too much Fluvoxamine Maleate Tablets, call your healthcare provider or poison control center right away, or get emergency treatment.

What should I avoid while taking Fluvoxamine Maleate Tablets?

Fluvoxamine Maleate Tablets can cause sleepiness or may affect your ability to make decisions, think clearly, or react quickly. You should not drive, operate heavy machinery, or do other dangerous activities until you know how Fluvoxamine Maleate Tablets affects you. Do not drink alcohol while using Fluvoxamine Maleate Tablets.

What are the possible side effects of Fluvoxamine Maleate Tablets?

Fluvoxamine Maleate Tablets may cause serious side effects, including:

- See “What is the most important information I should know about Fluvoxamine Maleate Tablets?”
- Feeling anxious or trouble sleeping

Common possible side effects in people who take Fluvoxamine Maleate Tablets include:

- nausea
- sleepiness
- weakness
- indigestion
- sweating
- loss of appetite
- shaking
- vomiting
- delayed ejaculation
- inability to have an orgasm
- decreased sex drive
- dry mouth
- stuffy nose
- unusual taste
- frequent urination

Other side effects in children and adolescents include:

- agitation or abnormal increase in activity
- feeling depressed or sad
- excessive gas
- heavy menstrual periods
- rash
- possible slowed growth rate and weight change

Tell your healthcare provider if you have any side effect that bothers you or that does not go away. These are not all the possible side effects of Fluvoxamine Maleate Tablets. For more information, ask your healthcare provider or pharmacist.

CALL YOUR DOCTOR FOR MEDICAL ADVICE ABOUT SIDE EFFECTS. YOU MAY REPORT SIDE EFFECTS at 1-855-204-1431 or FDA at 1-800-FDA-1088.

How should I store Fluvoxamine Maleate Tablets?

Store Fluvoxamine Maleate Tablets at room temperature between 59°F to 86°F (15°C to 30°C).

- Keep Fluvoxamine Maleate Tablets away from high humidity.
- Keep Fluvoxamine Maleate Tablets bottle closed tightly.

Keep Fluvoxamine Maleate Tablets and all medicines out of the reach of children.

General information about Fluvoxamine Maleate Tablets

Medicines are sometimes prescribed for purposes other than those listed in a Medication Guide. Do not use Fluvoxamine Maleate Tablets for a condition for which it was not prescribed. Do not give Fluvoxamine Maleate Tablets to other people, even if they have the same condition. It may harm them.

This Medication Guide summarizes the most important information about Fluvoxamine Maleate Tablets. If you would like more information, talk with your healthcare provider. You may ask your healthcare provider or pharmacist for information about Fluvoxamine Maleate Tablets that is written for healthcare professionals.

For more information about Fluvoxamine Maleate Tablets call toll free at 1-855-204-1431 or go to www.anipharmaceuticals.com.

What are the ingredients in Fluvoxamine Maleate Tablets?

Active ingredient: Fluvoxamine maleate

Inactive ingredients:

The 25 mg tablets: mannitol, polyethylene glycol, polyvinyl alcohol, pregelatinized starch (potato), silicon dioxide, sodium stearyl fumarate, starch (corn), talc, and titanium dioxide.

The 50 mg and 100 mg tablets: In addition to the above inactive ingredients, contain synthetic iron oxides.

All brand names listed are the registered trademarks of their respective owners and are not trademarks of ANI Pharmaceuticals, Inc.

This Medication Guide has been approved by the U.S. Food and Drug Administration.

Repackaged and Distributed By:

Remedy Repack, Inc.

625 Kolter Dr. Suite #4 Indiana, PA 1-724-465-8762

PACKAGE LABEL

DRUG: fluvoxamine maleate

GENERIC: Fluvoxamine maleate

DOSAGE: TABLET, COATED

ADMINSTRATION: ORAL

NDC: 70518-1643-0

COLOR: yellow

SHAPE: OVAL

SCORE: Two even pieces

SIZE: 12 mm

IMPRINT: 1225

PACKAGING: 30 in 1 BLISTER PACK

ACTIVE INGREDIENT(S):

- FLUVOXAMINE MALEATE 50mg in 1

INACTIVE INGREDIENT(S):

- MANNITOL
- POLYETHYLENE GLYCOL 3350
- POLYVINYL ALCOHOL, UNSPECIFIED
- SILICON DIOXIDE
- SODIUM STEARYL FUMARATE
- STARCH, CORN
- STARCH, POTATO
- TALC
- TITANIUM DIOXIDE
- FERRIC OXIDE YELLOW